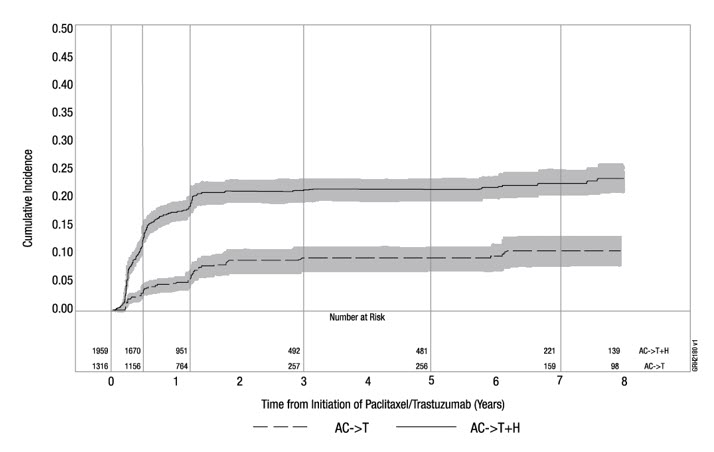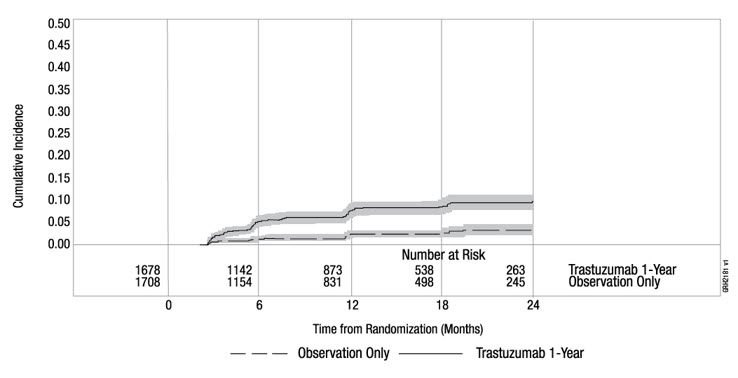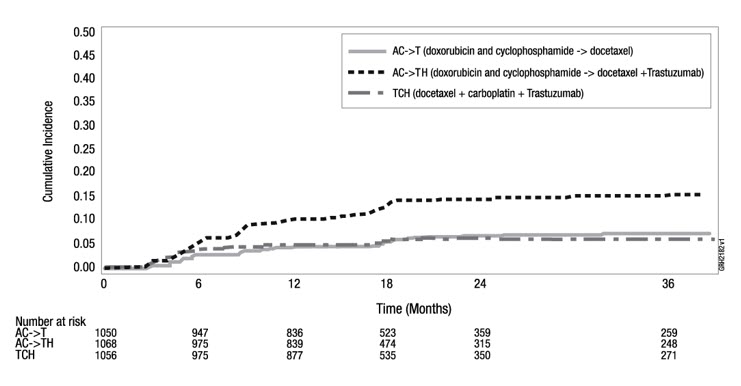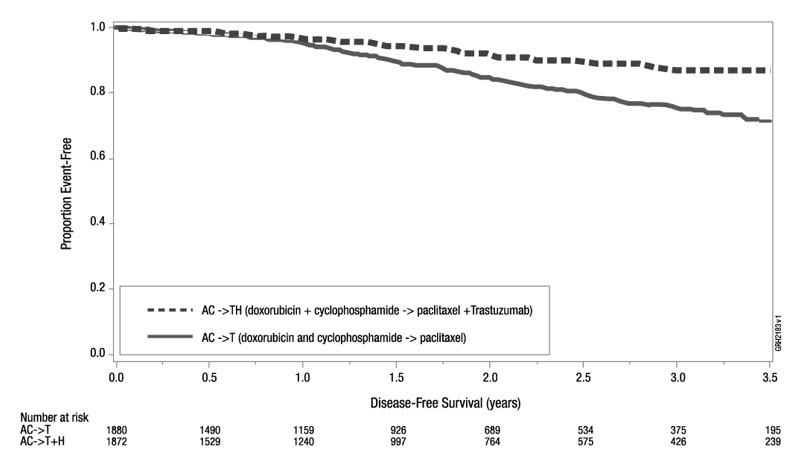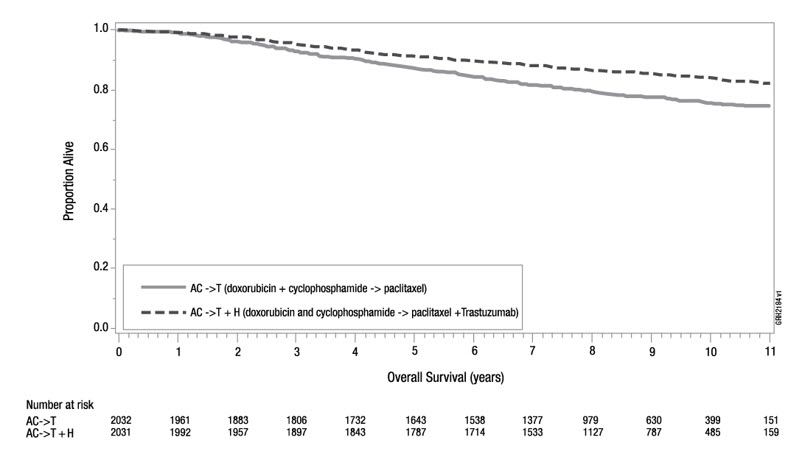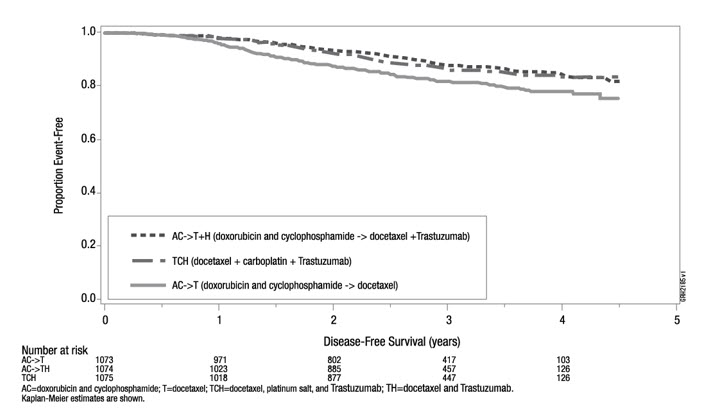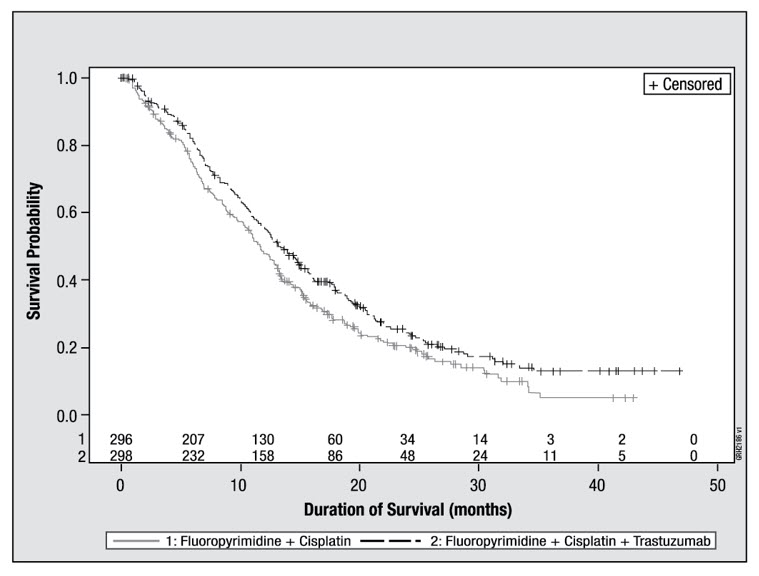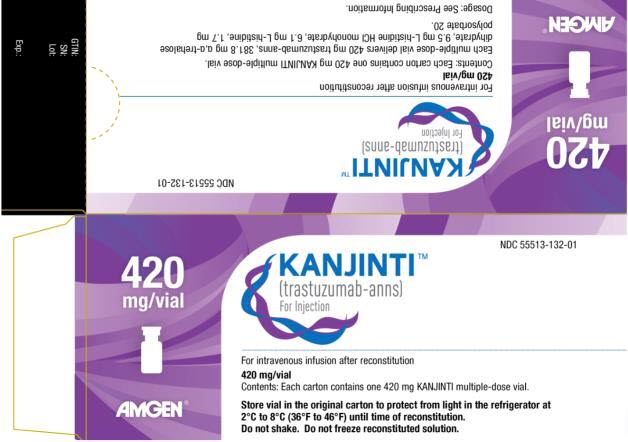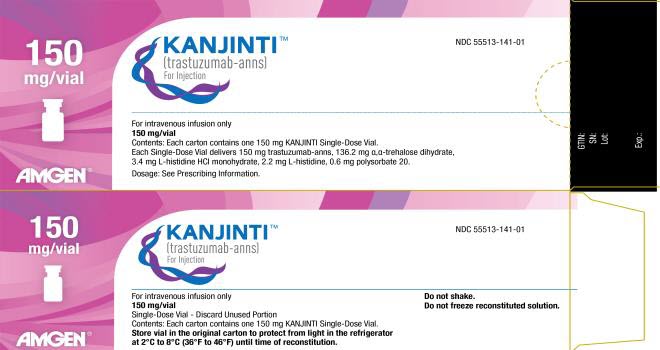 DRUG LABEL: Kanjinti
NDC: 55513-132 | Form: INJECTION, POWDER, LYOPHILIZED, FOR SOLUTION
Manufacturer: Amgen, Inc
Category: prescription | Type: HUMAN PRESCRIPTION DRUG LABEL
Date: 20250711

ACTIVE INGREDIENTS: TRASTUZUMAB 420 mg/20 mL
INACTIVE INGREDIENTS: TREHALOSE DIHYDRATE 381.8 mg/20 mL; HISTIDINE HYDROCHLORIDE MONOHYDRATE 9.5 mg/20 mL; HISTIDINE 6.1 mg/20 mL; POLYSORBATE 20 1.7 mg/20 mL

HIGHLIGHTS OF PRESCRIBING INFORMATION

These highlights do not include all the information needed to use KANJINTI safely and effectively. See full prescribing information for KANJINTI.
KANJINTI® (trastuzumab-anns) for injection, for intravenous use
Initial U.S. Approval: 2019
KANJINTI (trastuzumab-anns) is biosimilar [Biosimilar means that the biological product is approved based on data demonstrating that it is highly similar to an FDA-approved biological product, known as a reference product, and that there are no clinically meaningful differences between the biosimilar product and the reference product. Biosimilarity of KANJINTI has been demonstrated for the condition(s) of use (e.g. indication(s), dosing regimen(s)), strength(s), dosage form(s), and route(s) of administration described in its Full Prescribing Information.] to HERCEPTIN® (trastuzumab).

WARNING: CARDIOMYOPATHY, INFUSION REACTIONS, EMBRYO-FETAL TOXICITY, and PULMONARY TOXICITY

See full prescribing information for complete boxed warning

Cardiomyopathy: Trastuzumab products can result in subclinical and clinical cardiac failure manifesting as CHF, and decreased LVEF, with greatest risk when administered concurrently with anthracyclines. Evaluate cardiac function prior to and during treatment. Discontinue KANJINTI for cardiomyopathy. (2.5, 5.1)

Infusion Reactions, Pulmonary Toxicity: Discontinue KANJINTI for anaphylaxis, angioedema, interstitial pneumonitis, or acute respiratory distress syndrome. (5.2, 5.4)

Embryo-Fetal Toxicity: Exposure to trastuzumab products during pregnancy can result in oligohydramnios, in some cases complicated by pulmonary hypoplasia and neonatal death. Advise patients of these risks and the need for effective contraception. (5.3, 8.1, 8.3)

RECENT MAJOR CHANGES

Dosage and Administration, Evaluation and Testing Before Initiating KANJINTI (2.1) | 12/2024

1 INDICATIONS AND USAGE

KANJINTI is a HER2/neu receptor antagonist indicated in adults for:

- the treatment of HER2-overexpressing breast cancer. (1.1, 1.2)
- the treatment of HER2-overexpressing metastatic gastric or gastroesophageal junction adenocarcinoma. (1.3)

Select patients for therapy based on an FDA-approved companion diagnostic for a trastuzumab product (1, 2.2).

2 DOSAGE AND ADMINISTRATION

For intravenous (IV) infusion only. Do not administer as an IV push or bolus. KANJINTI has different dosage and administration instructions than subcutaneous trastuzumab products. (2.3)

Do not substitute KANJINTI (trastuzumab-anns) for or with ado-trastuzumab emtansine or fam-trastuzumab deruxtecan. (2.3)

Perform HER2 testing using FDA-approved tests by laboratories with demonstrated proficiency. (1, 2.2)

Adjuvant Treatment of HER2-Overexpressing Breast Cancer (2.2)

Administer at either:

- Initial dose of 4 mg/kg over 90 minutes IV infusion, then 2 mg/kg over 30 minutes IV infusion weekly for 12 weeks (with paclitaxel or docetaxel) or 18 weeks (with docetaxel and carboplatin). One week after the last weekly dose of KANJINTI, administer 6 mg/kg as an IV infusion over 30−90 minutes every three weeks to complete a total of 52 weeks of therapy, or
- Initial dose of 8 mg/kg over 90 minutes IV infusion, then 6 mg/kg over 30–90 minutes IV infusion every three weeks for 52 weeks.

Metastatic HER2-Overexpressing Breast Cancer (2.3)

- Initial dose of 4 mg/kg as a 90 minutes IV infusion followed by subsequent weekly doses of 2 mg/kg as 30 minutes IV infusions.

Metastatic HER2-Overexpressing Gastric Cancer (2.3)

- Initial dose of 8 mg/kg over 90 minutes IV infusion, followed by 6 mg/kg over 30 to 90 minutes IV infusion every 3 weeks.

3 DOSAGE FORMS AND STRENGTHS

- For Injection: 150 mg lyophilized powder in a single-dose vial for reconstitution
- For Injection: 420 mg lyophilized powder in a multiple-dose vial for reconstitution

4 CONTRAINDICATIONS

- None. (4)

5 WARNINGS AND PRECAUTIONS

- Exacerbation of Chemotherapy-Induced Neutropenia. (5.5, 6.1)

6 ADVERSE REACTIONS

Adjuvant Breast Cancer

- Most common adverse reactions (≥ 5%) are headache, diarrhea, nausea, and chills. (6.1)

Metastatic Breast Cancer

- Most common adverse reactions (≥ 10%) are fever, chills, headache, infection, congestive heart failure, insomnia, cough, and rash. (6.1)

Metastatic Gastric Cancer

- Most common adverse reactions (≥ 10%) are neutropenia, diarrhea, fatigue, anemia, stomatitis, weight loss, upper respiratory tract infections, fever, thrombocytopenia, mucosal inflammation, nasopharyngitis, and dysgeusia. (6.1)

To report SUSPECTED ADVERSE REACTIONS, contact Amgen Medical Information at 1-800-77-AMGEN (1-800-772-6436) or FDA at 1-800-FDA-1088 or www.fda.gov/medwatch.

8 USE IN SPECIFIC POPULATIONS

Females and Males of Reproductive Potential: Verify the pregnancy status of females prior to initiation of KANJINTI (8.3).

FULL PRESCRIBING INFORMATION

WARNING: CARDIOMYOPATHY, INFUSION REACTIONS, EMBRYO-FETAL TOXICITY, and PULMONARY TOXICITY

Cardiomyopathy

Administration of trastuzumab products can result in sub-clinical and clinical cardiac failure. The incidence and severity was highest in patients receiving trastuzumab with anthracycline-containing chemotherapy regimens.

Evaluate left ventricular function in all patients prior to and during treatment with KANJINTI. Discontinue KANJINTI treatment in patients receiving adjuvant therapy and withhold KANJINTI in patients with metastatic disease for clinically significant decrease in left ventricular function [see Dosage and Administration (2.5) and Warnings and Precautions (5.1)].

Infusion Reactions; Pulmonary Toxicity

Administration of trastuzumab products can result in serious and fatal infusion reactions and pulmonary toxicity. Symptoms usually occur during or within 24 hours of administration of trastuzumab products. Interrupt KANJINTI infusion for dyspnea or clinically significant hypotension. Monitor patients until symptoms completely resolve. Discontinue KANJINTI for anaphylaxis, angioedema, interstitial pneumonitis, or acute respiratory distress syndrome [see Warnings and Precautions (5.2, 5.4)].

Embryo-Fetal Toxicity

Exposure to trastuzumab products during pregnancy can result in oligohydramnios and oligohydramnios sequence manifesting as pulmonary hypoplasia, skeletal abnormalities, and neonatal death. Advise patients of these risks and the need for effective contraception [see Warnings and Precautions (5.3) and Use in Specific Populations (8.1, 8.3)].

1 INDICATIONS AND USAGE

1.1 Adjuvant Breast Cancer

KANJINTI is indicated in adults for adjuvant treatment of HER2-overexpressing node positive or node negative (ER/PR negative or with one high risk feature [see Clinical Studies (14.1)]) breast cancer

- as part of a treatment regimen consisting of doxorubicin, cyclophosphamide, and either paclitaxel or docetaxel
- as part of a treatment regimen with docetaxel and carboplatin
- as a single agent following multi-modality anthracycline-based therapy.

Select patients for therapy based on an FDA-approved companion diagnostic for a trastuzumab product [see Dosage and Administration (2.2)].

1.2 Metastatic Breast Cancer

KANJINTI is indicated in adults:

- In combination with paclitaxel for first-line treatment of HER2-overexpressing metastatic breast cancer
- As a single agent for treatment of HER2-overexpressing breast cancer in patients who have received one or more chemotherapy regimens for metastatic disease.

Select patients for therapy based on an FDA-approved companion diagnostic for a trastuzumab product [see Dosage and Administration (2.2)]

1.3 Metastatic Gastric Cancer

KANJINTI is indicated in adults, in combination with cisplatin and capecitabine or 5-fluorouracil, for the treatment of patients with HER2-overexpressing metastatic gastric or gastroesophageal junction adenocarcinoma who have not received prior treatment for metastatic disease.

Select patients for therapy based on an FDA-approved companion diagnostic for a trastuzumab product [see Dosage and Administration (2.2)].

2 DOSAGE AND ADMINISTRATION

2.1 Evaluation and Testing Before Initiating KANJINTI

Assess left ventricular ejection fraction (LVEF) prior to initiation of KANJINTI and at regular intervals during treatment [see Boxed Warning, Dosage and Administration (2.5), Warnings and Precautions (5.1)].

Verify the pregnancy status of females of reproductive potential prior to the initiation of KANJINTI [see Warnings and Precautions (5.3), Use in Specific Populations (8.1, 8.3)].

2.2 Patient Selection

Select patients based on HER2 protein overexpression or HER2 gene amplification in tumor specimens [see Indications and Usage (1) and Clinical Studies (14)]. Assessment of HER2 protein overexpression and HER2 gene amplification should be performed using FDA-approved tests specific for breast or gastric cancers by laboratories with demonstrated proficiency. Information on the FDA-approved tests for the detection of HER2 protein overexpression and HER2 gene amplification is available at: http://www.fda.gov/CompanionDiagnostics.

Assessment of HER2 protein overexpression and HER2 gene amplification in metastatic gastric cancer should be performed using FDA-approved tests specifically for gastric cancers due to differences in gastric vs. breast histopathology, including incomplete membrane staining and more frequent heterogeneous expression of HER2 seen in gastric cancers.

Improper assay performance, including use of suboptimally fixed tissue, failure to utilize specified reagents, deviation from specific assay instructions, and failure to include appropriate controls for assay validation, can lead to unreliable results.

2.3 Recommended Dosage

- KANJINTI is for intravenous infusion only. Do not administer as an intravenous push or bolus.
- KANJINTI has different dosage and administration instructions than subcutaneous trastuzumab products.
- Do not mix KANJINTI with other drugs.
- Do not substitute KANJINTI (trastuzumab-anns) for or with ado-trastuzumab emtansine or fam-trastuzumab deruxtecan.

Adjuvant Treatment of Breast Cancer:

Administer according to one of the following doses and schedules for a total of 52 weeks of KANJINTI therapy:

During and following paclitaxel, docetaxel, or docetaxel and carboplatin:

- Initial dose of 4 mg/kg as an intravenous infusion over 90 minutes then at 2 mg/kg as an intravenous infusion over 30 minutes weekly during chemotherapy for the first 12 weeks (paclitaxel or docetaxel) or 18 weeks (docetaxel and carboplatin).
- One week following the last weekly dose of KANJINTI, administer KANJINTI at 6 mg/kg as an intravenous infusion over 30–90 minutes every three weeks.

As a single agent within three weeks following completion of multi-modality, anthracycline-based chemotherapy regimens:

- Initial dose at 8 mg/kg as an intravenous infusion over 90 minutes.
- Subsequent doses at 6 mg/kg as an intravenous infusion over 30-90 minutes every three weeks.
- Extending adjuvant treatment beyond one year is not recommended [see Adverse Reactions (6.1)].

Metastatic Breast Cancer:

- Administer KANJINTI, alone or in combination with paclitaxel, at an initial dose of 4 mg/kg as a 90-minute intravenous infusion followed by subsequent once weekly doses of 2 mg/kg as 30-minute intravenous infusions until disease progression.

Metastatic Gastric Cancer:

- Administer KANJINTI at an initial dose of 8 mg/kg as a 90-minute intravenous infusion followed by subsequent doses of 6 mg/kg as an intravenous infusion over 30-90 minutes every three weeks until disease progression.

2.4 Important Dosing Considerations

Missed Dose

If the patient has missed a dose of KANJINTI by one week or less, then the usual maintenance dose (weekly schedule: 2 mg/kg; once every three weeks schedule: 6 mg/kg) should be administered as soon as possible. Do not wait until the next planned cycle. Subsequent KANJINTI maintenance doses should be administered 7 days or 21 days later according to the weekly or once every three week schedules, respectively.

If the patient has missed a dose of KANJINTI by more than one week, a re-loading dose of KANJINTI should be administered over approximately 90 minutes (weekly schedule: 4 mg/kg; once every three week schedule: 8 mg/kg) as soon as possible. Subsequent KANJINTI maintenance doses (weekly schedule: 2 mg/kg; three-weekly schedule 6 mg/kg) should be administered 7 days or 21 days later according to the weekly or once every three week schedules, respectively.

2.5 Dosage Modifications for Adverse Reactions

Infusion Reactions

[see Boxed Warning, Warnings and Precautions (5.2)]

- Decrease the rate of infusion for mild or moderate infusion reactions
- Interrupt the infusion in patients with dyspnea or clinically significant hypotension
- Discontinue KANJINTI for severe or life-threatening infusion reactions.

Cardiomyopathy

[see Boxed Warning, Warnings and Precautions (5.1)]

Assess left ventricular ejection fraction (LVEF) prior to initiation of KANJINTI and at regular intervals during treatment. Withhold KANJINTI dosing for at least 4 weeks for either of the following:

- ≥ 16% absolute decrease in LVEF from pre-treatment values
- LVEF below institutional limits of normal and ≥ 10% absolute decrease in LVEF from pre-treatment values.

KANJINTI may be resumed if, within 4–8 weeks, the LVEF returns to normal limits and the absolute decrease from baseline is ≤ 15%.

Permanently discontinue KANJINTI for a persistent (> 8 weeks) LVEF decline or for suspension of KANJINTI dosing on more than 3 occasions for cardiomyopathy.

2.6 Preparation Instructions

To prevent medication errors, it is important to check the vial labels to ensure that the drug being prepared and administered is KANJINTI (trastuzumab-anns) and not ado-trastuzumab emtansine or fam-trastuzumab deruxtecan.

420 mg Multiple-dose vial

Reconstitution

Reconstitute each 420 mg vial of KANJINTI with 20 mL of Bacteriostatic Water for Injection (BWFI), USP, containing 0.9% to 1.1% benzyl alcohol as a preservative to yield a multiple-dose solution containing 21 mg/mL trastuzumab-anns that delivers 20 mL (420 mg trastuzumab-anns). In patients with known hypersensitivity to benzyl alcohol, reconstitute with 20 mL of Sterile Water for Injection (SWFI) without preservative to yield a one-time use solution.

Use appropriate aseptic technique when performing the following reconstitution steps:

- Using a sterile syringe, slowly inject the 20 mL of diluent into the vial containing the lyophilized powder of KANJINTI, which has a cake-like appearance. The stream of diluent should be directed into the cake. The reconstituted vial yields a solution for multiple-dose use, containing 21 mg/mL trastuzumab-anns.
- Swirl the vial gently to aid reconstitution. DO NOT SHAKE.
- Slight foaming of the product may be present upon reconstitution. Allow the vial to stand undisturbed for approximately 5 minutes.
- Parenteral drug products should be inspected visually for particulate matter and discoloration prior to administration, whenever solution and container permit. Inspect visually for particulates and discoloration. The solution should be free of visible particulates, clear to slightly opalescent and colorless to pale yellow.
- Store reconstituted KANJINTI in the refrigerator at 2°C to 8°C (36°F to 46°F); discard unused KANJINTI after 28 days. If KANJINTI is reconstituted with SWFI without preservative, use immediately and discard any unused portion. Do not freeze.

Dilution

- Determine the dose (mg) of KANJINTI [see Dosage and Administration (2.3)]. Calculate the volume of the 21 mg/mL reconstituted KANJINTI solution needed, withdraw this amount from the vial using a sterile needle and syringe and add it to an infusion bag containing 250 mL of 0.9% Sodium Chloride Injection, USP.
  DO NOT USE DEXTROSE (5%) SOLUTION.
- Gently invert the bag to mix the solution.
- The solution of KANJINTI for infusion diluted in polyvinylchloride or polyethylene bags containing 0.9% Sodium Chloride Injection, USP, should be stored at 2°C to 8°C (36°F to 46°F) for no more than 24 hours prior to use. This storage time is additional to the time allowed for the reconstituted vials. Do not freeze.

150 mg Single-dose vial

Reconstitution

Reconstitute each 150 mg vial of KANJINTI with 7.4 mL of Sterile Water for Injection (SWFI) (not supplied) to yield a single-dose solution containing 21 mg/mL trastuzumab-anns that delivers 7.15 mL (150 mg trastuzumab-anns).

Use appropriate aseptic technique when performing the following reconstitution steps:

- Using a sterile syringe, slowly inject 7.4 mL of SWFI (not supplied) into the vial containing the lyophilized powder of KANJINTI, which has a cake-like appearance. The stream of diluent should be directed into the cake. The reconstituted vial yields a solution containing 21 mg/mL trastuzumab-anns.
- Swirl the vial gently to aid reconstitution. DO NOT SHAKE.
- Slight foaming of the product may be present upon reconstitution. Allow the vial to stand undisturbed for approximately 5 minutes.
- Parenteral drug products should be inspected visually for particulate matter and discoloration prior to administration, whenever solution and container permit. Inspect visually for particulates and discoloration. The solution should be free of visible particulates, clear to slightly opalescent and colorless to pale yellow.
- Use the KANJINTI solution immediately following reconstitution with SWFI, as it contains no preservatives and is intended for one-time use only. If not used immediately, store the reconstituted KANJINTI solution for up to 24 hours at 2°C to 8°C (36°F to 46°F); discard any unused KANJINTI after 24 hours. Do not freeze.

Dilution

- Determine the dose (mg) of KANJINTI [see Dosage and Administration (2.3)].
- Calculate the volume of the 21 mg/mL reconstituted KANJINTI solution needed.
- Withdraw this amount from the vial using a sterile needle and syringe and add it to an infusion bag containing 250 mL of 0.9% Sodium Chloride Injection, USP. DO NOT USE DEXTROSE 5% SOLUTION.
- Gently invert the bag to mix the solution.
- The solution of KANJINTI for infusion diluted in polyvinylchloride or polyethylene bags containing 0.9% Sodium Chloride Injection, USP, should be stored at 2°C to 8°C (36°F to 46°F) for no more than 24 hours prior to use. Discard after 24 hours. This storage time is additional to the time allowed for the reconstituted vials. Do not freeze.

3 DOSAGE FORMS AND STRENGTHS

- For injection: 150 mg of KANJINTI as a white to pale yellow lyophilized powder in a single-dose vial.
- For injection: 420 mg of KANJINTI as a white to pale yellow lyophilized powder in a multiple-dose vial.

4 CONTRAINDICATIONS

None.

5 WARNINGS AND PRECAUTIONS

5.1 Cardiomyopathy

Trastuzumab products can cause left ventricular cardiac dysfunction, arrhythmias, hypertension, disabling cardiac failure, cardiomyopathy, and cardiac death [see Boxed Warning: Cardiomyopathy]. Trastuzumab products can also cause asymptomatic decline in left ventricular ejection fraction (LVEF).

There is a 4–6 fold increase in the incidence of symptomatic myocardial dysfunction among patients receiving trastuzumab products as a single agent or in combination therapy compared with those not receiving trastuzumab products. The highest absolute incidence occurs when a trastuzumab product is administered with an anthracycline.

Withhold KANJINTI for ≥ 16% absolute decrease in LVEF from pre-treatment values or an LVEF value below institutional limits of normal and ≥ 10% absolute decrease in LVEF from pretreatment values [see Dosage and Administration (2.5)]. The safety of continuation or resumption of trastuzumab products in patients with trastuzumab product-induced left ventricular cardiac dysfunction has not been studied.

Patients who receive anthracycline after stopping trastuzumab products may also be at increased risk of cardiac dysfunction [see Drug Interactions (7) and Clinical Pharmacology (12.3)].

Cardiac Monitoring

Conduct thorough cardiac assessment, including history, physical examination, and determination of LVEF by echocardiogram or MUGA scan. The following schedule is recommended:

- Baseline LVEF measurement immediately prior to initiation of KANJINTI
- LVEF measurements every 3 months during and upon completion of KANJINTI
- Repeat LVEF measurement at 4-week intervals if KANJINTI is withheld for significant left ventricular cardiac dysfunction [see Dosage and Administration (2.5)]
- LVEF measurements every 6 months for at least 2 years following completion of KANJINTI as a component of adjuvant therapy.

In NSABP B31, 15% (158/1031) of patients discontinued trastuzumab due to clinical evidence of myocardial dysfunction or significant decline in LVEF after a median follow-up duration of 8.7 years in the AC-TH (anthracycline, cyclophosphamide, paclitaxel, and trastuzumab) arm. In HERA (one-year trastuzumab treatment), the number of patients who discontinued trastuzumab due to cardiac toxicity at 12.6 months median duration of follow-up was 2.6% (44/1678). In BCIRG006, a total of 2.9% (31/1056) of patients in the TCH (docetaxel, carboplatin, trastuzumab) arm (1.5% during the chemotherapy phase and 1.4% during the monotherapy phase) and 5.7% (61/1068) of patients in the AC-TH arm (1.5% during the chemotherapy phase and 4.2% during the monotherapy phase) discontinued trastuzumab due to cardiac toxicity.

Among 64 patients receiving adjuvant chemotherapy (NSABP B31 and NCCTG N9831) who developed congestive heart failure, one patient died of cardiomyopathy, one patient died suddenly without documented etiology and 33 patients were receiving cardiac medication at last follow-up. Approximately 24% of the surviving patients had recovery to a normal LVEF (defined as ≥ 50%) and no symptoms on continuing medical management at the time of last follow-up. Incidence of congestive heart failure (CHF) is presented in Table 1. The safety of continuation or resumption of trastuzumab products in patients with trastuzumab product-induced left ventricular cardiac dysfunction has not been studied.

Table 1. Incidence of Congestive Heart Failure in Adjuvant Breast Cancer Studies
Study | Regimen | Incidence of Congestive Heart Failure % (n)
Study | Regimen | Trastuzumab | Control
NSABP B31 & NCCTG N9831 [Median follow-up duration for NSABP B31 & NCCTG N9831 combined was 8.3 years in the AC→paclitaxel + trastuzumab arm.] | AC [Anthracycline (doxorubicin) and cyclophosphamide.] → Paclitaxel + Trastuzumab | 3.2% (64/2000) [Includes 1 patient with fatal cardiomyopathy and 1 patient with sudden death without documented etiology.] | 1.3% (21/1655)
HERA [Includes NYHA II-IV and cardiac death at 12.6 months median duration of follow-up in the one-year trastuzumab arm.] | Chemotherapy → Trastuzumab | 2% (30/1678) | 0.3% (5/1708)
BCIRG006 | AC→Docetaxel + Trastuzumab | 2% (20/1068) | 0.3% (3/1050)
BCIRG006 | Docetaxel + Carboplatin + Trastuzumab | 0.4% (4/1056) | 0.3% (3/1050)

In HERA (one-year trastuzumab treatment), at a median follow-up duration of 8 years, the incidence of severe CHF (NYHA III & IV) was 0.8%, and the rate of mild symptomatic and asymptomatic left ventricular dysfunction was 4.6%.

Table 2. Incidence of Cardiac Dysfunction [Congestive heart failure or significant asymptomatic decrease in LVEF.] in Metastatic Breast Cancer Studies
 |  | Incidence
 |  | NYHA I-IV |  | NYHA III-IV
Study | Event | Trastuzumab | Control | Trastuzumab | Control
H0648g (AC) [Anthracycline (doxorubicin or epirubicin) and cyclophosphamide.] | Cardiac Dysfunction | 28% | 7% | 19% | 3%
H0648g (paclitaxel) | Cardiac Dysfunction | 11% | 1% | 4% | 1%
H0649g | Cardiac Dysfunction [Includes 1 patient with fatal cardiomyopathy.] | 7% | N/A | 5% | N/A

In BCIRG006, the incidence of NCI-CTC Grade 3/4 cardiac ischemia/infarction was higher in the trastuzumab-containing regimens (AC-TH: 0.3% (3/1068) and TCH: 0.2% (2/1056)) as compared to none in AC-T.

5.2 Infusion Reactions

Infusion reactions consist of a symptom complex characterized by fever and chills, and on occasion included nausea, vomiting, pain (in some cases at tumor sites), headache, dizziness, dyspnea, hypotension, rash, and asthenia [see Adverse Reactions (6.1)].

In post-marketing reports, serious and fatal infusion reactions have been reported. Severe reactions, which include bronchospasm, anaphylaxis, angioedema, hypoxia, and severe hypotension, were usually reported during or immediately following the initial infusion. However, the onset and clinical course were variable, including progressive worsening, initial improvement followed by clinical deterioration, or delayed post-infusion events with rapid clinical deterioration. For fatal events, death occurred within hours to days following a serious infusion reaction.

Interrupt KANJINTI infusion in all patients experiencing dyspnea, clinically significant hypotension, and intervention of medical therapy administered (which may include epinephrine, corticosteroids, diphenhydramine, bronchodilators, and oxygen). Patients should be evaluated and carefully monitored until complete resolution of signs and symptoms. Permanent discontinuation should be strongly considered in all patients with severe infusion reactions.

There are no data regarding the most appropriate method of identification of patients who may safely be retreated with trastuzumab products after experiencing a severe infusion reaction. Prior to resumption of trastuzumab infusion, the majority of patients who experienced a severe infusion reaction were pre-medicated with antihistamines and/or corticosteroids. While some patients tolerated trastuzumab infusions, others had recurrent severe infusion reactions despite pre-medications.

5.3 Embryo-Fetal Toxicity

Trastuzumab products can cause fetal harm when administered to a pregnant woman. In post-marketing reports, use of trastuzumab during pregnancy resulted in cases of oligohydramnios and oligohydramnios sequence manifesting as pulmonary hypoplasia, skeletal abnormalities, and neonatal death.

Verify the pregnancy status of females of reproductive potential prior to the initiation of KANJINTI. Advise pregnant women and females of reproductive potential that exposure to KANJINTI during pregnancy or within 7 months prior to conception can result in fetal harm. Advise females of reproductive potential to use effective contraception during treatment and for 7 months following the last dose of KANJINTI [see Use in Specific Populations (8.1, 8.3) and Clinical Pharmacology (12.3)].

5.4 Pulmonary Toxicity

Trastuzumab product use can result in serious and fatal pulmonary toxicity. Pulmonary toxicity includes dyspnea, interstitial pneumonitis, pulmonary infiltrates, pleural effusions, non-cardiogenic pulmonary edema, pulmonary insufficiency and hypoxia, acute respiratory distress syndrome, and pulmonary fibrosis. Such events can occur as sequelae of infusion reactions [see Warnings and Precautions (5.2)]. Patients with symptomatic intrinsic lung disease or with extensive tumor involvement of the lungs, resulting in dyspnea at rest, appear to have more severe toxicity.

5.5 Exacerbation of Chemotherapy-Induced Neutropenia

In randomized, controlled clinical trials, the per-patient incidences of NCI-CTC Grade 3–4 neutropenia and of febrile neutropenia were higher in patients receiving trastuzumab in combination with myelosuppressive chemotherapy as compared to those who received chemotherapy alone. The incidence of septic death was similar among patients who received trastuzumab and those who did not [see Adverse Reactions (6.1)].

6 ADVERSE REACTIONS

The following adverse reactions are discussed in greater detail in other sections of the label:

- Cardiomyopathy [see Warnings and Precautions (5.1)]
- Infusion Reactions [see Warnings and Precautions (5.2)]
- Embryo-Fetal Toxicity [see Warnings and Precautions (5.3)]
- Pulmonary Toxicity [see Warnings and Precautions (5.4)]
- Exacerbation of Chemotherapy-Induced Neutropenia [see Warnings and Precautions (5.5)]

6.1 Clinical Trials Experience

Because clinical trials are conducted under widely varying conditions, adverse reaction rates observed in the clinical trials of a drug cannot be directly compared to rates in the clinical trials of another drug and may not reflect the rates observed in practice.

The most common adverse reactions in patients receiving trastuzumab products in the adjuvant and metastatic breast cancer setting are fever, nausea, vomiting, infusion reactions, diarrhea, infections, increased cough, headache, fatigue, dyspnea, rash, neutropenia, anemia, and myalgia. Adverse reactions requiring interruption or discontinuation of trastuzumab product treatment include CHF, significant decline in left ventricular cardiac function, severe infusion reactions, and pulmonary toxicity [see Dosage and Administration (2.5)].

In the metastatic gastric cancer setting, the most common adverse reactions (≥ 10%) that were increased (≥ 5% difference) in the trastuzumab arm as compared to the chemotherapy alone arm were neutropenia, diarrhea, fatigue, anemia, stomatitis, weight loss, upper respiratory tract infections, fever, thrombocytopenia, mucosal inflammation, nasopharyngitis, and dysgeusia.

The most common adverse reactions which resulted in discontinuation of treatment on the trastuzumab-containing arm in the absence of disease progression were infection, diarrhea, and febrile neutropenia.

Adjuvant Breast Cancer

The information below reflects exposure to one-year trastuzumab therapy across three randomized, open-label studies, NSABP B31, NCCTG N9831, and HERA, with (n = 3678) or without (n = 3363) trastuzumab in the adjuvant treatment of breast cancer.

HERA

Table 3 reflects exposure to trastuzumab in 1678 patients in HERA; the median treatment duration was 51 weeks and median number of infusions was 18 [see Clinical Studies (14.1)].

Table 3. Adverse Reactions (≥ 1%) in HERA (All Grades) [The incidence of Grade 3 or higher adverse reactions was < 1% in both arms for each listed term.]
Adverse Reactions | Trastuzumab (n = 1678) % | Observation (n = 1708) %
Nervous System
Headache | 10 | 3
Paresthesia | 2 | 0.6
Musculoskeletal
Arthralgia | 8 | 6
Back Pain | 5 | 3
Myalgia | 4 | 1
Bone Pain | 3 | 2
Muscle Spasm | 3 | 0.2
Infections
Nasopharyngitis | 8 | 3
Urinary tract infection | 3 | 0.8
Gastrointestinal
Diarrhea | 7 | 1
Nausea | 6 | 1
Vomiting | 3.5 | 0.6
Constipation | 2 | 1
Dyspepsia | 2 | 0.5
Upper abdominal pain | 2 | 1
General
Pyrexia | 6 | 0.4
Peripheral edema | 5 | 2
Chills | 5 | 0
Asthenia | 4.5 | 2
Influenza-like illness | 2 | 0.2
Respiratory Thoracic Mediastinal
Cough | 5 | 2
Influenza | 4 | 0.5
Dyspnea | 3 | 2
URI | 3 | 1
Rhinitis | 2 | 0.4
Pharyngolaryngeal pain | 2 | 0.5
Sinusitis | 2 | 0.3
Epistaxis | 2 | 0.06
Cardiac
Hypertension | 4 | 2
Dizziness | 4 | 2
Ejection fraction decreased | 3.5 | 0.6
Palpitations | 3 | 0.7
Cardiac arrhythmias [Higher level grouping term.] | 3 | 1
Cardiac failure (congestive) | 2 | 0.3
Skin & Subcutaneous Tissue
Rash | 4 | 0.6
Nail disorders | 2 | 0
Pruritus | 2 | 0.6

Clinically relevant adverse reactions in < 1% of patients who received trastuzumab in HERA included hypersensitivity (0.6%), cardiac failure (0.5%), cardiac disorder (0.3%), interstitial pneumonitis (0.2%), pulmonary hypertension (0.2%), ventricular disorder (0.2%), autoimmune thyroiditis (0.3%), and sudden death (0.06%).

Adjuvant Treatment of Breast Cancer with Trastuzumab Beyond One Year

Extending adjuvant treatment beyond one year is not recommended [see Dosage and Administration (2.3)]. In HERA, a comparison of trastuzumab administered once every 3 weeks for two years versus one year was performed. The rate of asymptomatic cardiac dysfunction was increased in the 2-year trastuzumab compared to the 1-year trastuzumab treatment arm (8.1% versus 4.6%, respectively). More patients experienced at least one adverse reaction of Grade 3 or higher in the 2-year trastuzumab treatment arm (20.4%) compared with the one-year trastuzumab treatment arm (16.3%).

NSABP B31 and NCCTG N9831

The safety data from NSABP B31 and NCCTG N9831 were obtained from 3655 patients, of whom 2000 received trastuzumab; the median treatment duration was 51 weeks [see Clinical Studies (14.1)].

In NSABP B31, only Grade 3–5 adverse events, treatment-related Grade 2 events, and Grade 2–5 dyspnea were collected during and for up to 3 months following protocol-specified treatment. The following non-cardiac adverse reactions of Grade 2–5 occurred at an incidence of at least 2% greater among patients receiving trastuzumab plus chemotherapy as compared to chemotherapy alone: fatigue (29.5% vs. 22.4%), infection (24% vs. 12.8%), hot flashes (17.1% vs. 15%), anemia (12.3% vs. 6.7%), dyspnea (11.8% vs. 4.6%), rash/desquamation (10.9% vs. 7.6%), leukopenia (10.5% vs. 8.4%), neutropenia (6.4% vs. 4.3%), headache (6.2% vs. 3.8%), pain (5.5% vs. 3%), edema (4.7% vs. 2.7%) and insomnia (4.3% vs. 1.5%). The majority of these events were Grade 2 in severity.

In NCCTG N9831, data collection was limited to the following investigator-attributed treatment-related adverse reactions: NCI-CTC Grade 4 and 5 hematologic toxicities, Grade 3-5 non-hematologic toxicities, selected Grade 2–5 toxicities associated with taxanes (myalgia, arthralgias, nail changes, motor neuropathy, sensory neuropathy) and Grade 1–5 cardiac toxicities occurring during chemotherapy and/or trastuzumab treatment. The following non-cardiac adverse reactions of Grade 2–5 occurred at an incidence of at least 2% greater among patients receiving trastuzumab plus chemotherapy as compared to chemotherapy alone: arthralgia (12.2% vs. 9.1%), nail changes (11.5% vs.6.8%), dyspnea (2.4% vs. 0.2%), and diarrhea (2.2% vs. 0%). The majority of these events were Grade 2 in severity.

BCIRG006

Safety data from BCIRG006 reflect exposure to trastuzumab as part of an adjuvant treatment regimen from 2124 patients receiving at least one dose of study treatment [AC-TH: n = 1068; TCH: n = 1056]. The overall median treatment duration was 54 weeks in both the AC-TH and TCH arms. The median number of infusions was 26 in the AC-TH arm and 30 in the TCH arm, including weekly infusions during the chemotherapy phase and once every three week dosing in the monotherapy period [see Clinical Studies (14.1)]. In BCIRG006, the toxicity profile was similar to that reported in NSABP B31, NCCTG N9831, and HERA with the exception of a lower incidence of CHF in the TCH arm.

Metastatic Breast Cancer Studies

The safety of trastuzumab was evaluated in one randomized, open-label study (H0648g) of chemotherapy with (n = 235) or without (n = 234) intravenous trastuzumab in patients with metastatic breast cancer and in one single-arm study (H0649g) in patients with metastatic breast cancer (n = 222) [see Clinical Studies (14.1)]. Patients received 4 mg/kg initial dose of trastuzumab followed by 2 mg/kg weekly. In H0648g, 58% of patients received trastuzumab for ≥ 6 months and 9% received trastuzumab ≥ 12 months, respectively. In H0649g, 31% of patients received trastuzumab for ≥ 6 months and 16% received trastuzumab for ≥ 12 months, respectively.

Table 4 shows the adverse reactions (≥ 5%) in patients from H0648g and H0649g.

Table 4. Adverse Reactions (≥ 5%) in the Trastuzumab Arms in H0648g and H0649g
 | Trastuzumab [Data for trastuzumab single agent were from 4 studies, including 213 patients from H0649g.] n = 352 % | Trastuzumab + Paclitaxel n = 91 % | Paclitaxel n = 95 % | Trastuzumab + AC [Anthracycline (doxorubicin or epirubicin) and cyclophosphamide.] n = 143 % | AC n = 135 %
General
Pain | 47 | 61 | 62 | 57 | 42
Asthenia | 42 | 62 | 57 | 54 | 55
Fever | 36 | 49 | 23 | 56 | 34
Chills | 32 | 41 | 4 | 35 | 11
Headache | 26 | 36 | 28 | 44 | 31
Abdominal pain | 22 | 34 | 22 | 23 | 18
Back pain | 22 | 34 | 30 | 27 | 15
Infection | 20 | 47 | 27 | 47 | 31
Flu syndrome | 10 | 12 | 5 | 12 | 6
Accidental injury | 6 | 13 | 3 | 9 | 4
Allergic reaction | 3 | 8 | 2 | 4 | 2
Gastrointestinal
Nausea | 33 | 51 | 9 | 76 | 77
Diarrhea | 25 | 45 | 29 | 45 | 26
Vomiting | 23 | 37 | 28 | 53 | 49
Anorexia | 14 | 24 | 16 | 31 | 26
Nausea and vomiting | 8 | 14 | 11 | 18 | 9
Respiratory
Cough increased | 26 | 41 | 22 | 43 | 29
Dyspnea | 22 | 27 | 26 | 42 | 25
Rhinitis | 14 | 22 | 5 | 22 | 16
Pharyngitis | 12 | 22 | 14 | 30 | 18
Sinusitis | 9 | 21 | 7 | 13 | 6
Skin
Rash | 18 | 38 | 18 | 27 | 17
Herpes simplex | 2 | 12 | 3 | 7 | 9
Acne | 2 | 11 | 3 | 3 | < 1
Nervous
Insomnia | 14 | 25 | 13 | 29 | 15
Dizziness | 13 | 22 | 24 | 24 | 18
Paresthesia | 9 | 48 | 39 | 17 | 11
Depression | 6 | 12 | 13 | 20 | 12
Peripheral neuritis | 2 | 23 | 16 | 2 | 2
Neuropathy | 1 | 13 | 5 | 4 | 4
Metabolic
Peripheral edema | 10 | 22 | 20 | 20 | 17
Edema | 8 | 10 | 8 | 11 | 5
Cardiovascular
Congestive heart failure | 7 | 11 | 1 | 28 | 7
Tachycardia | 5 | 12 | 4 | 10 | 5
Musculoskeletal
Bone pain | 7 | 24 | 18 | 7 | 7
Arthralgia | 6 | 37 | 21 | 8 | 9
Urogenital
Urinary tract infection | 5 | 18 | 14 | 13 | 7
Blood and Lymphatic
Anemia | 4 | 14 | 9 | 36 | 26
Leukopenia | 3 | 24 | 17 | 52 | 34

Metastatic Gastric Cancer

The safety of trastuzumab was evaluated in patients with previously untreated metastatic gastric or gastroesophageal junction adenocarcinoma in an open-label, multicenter trial (ToGA) [see Clinical Studies (14.3)]. Patients were randomized (1:1) to receive trastuzumab in combination with cisplatin and a fluoropyrimidine (FC+H) (n = 294) or chemotherapy alone (FC) (n = 290). Patients in the trastuzumab plus chemotherapy arm received trastuzumab 8 mg/kg administered on Day 1 (prior to chemotherapy) followed by 6 mg/kg every 21 days until disease progression. Cisplatin was administered at 80 mg/m^2 on Day 1 and the fluoropyrimidine was administered as either capecitabine 1000 mg/m^2 orally twice a day on Days 1-14 or 5-fluorouracil 800 mg/m^2/day as a continuous intravenous infusion Days 1 through 5. Chemotherapy was administered for six 21-day cycles. Median duration of trastuzumab treatment was 21 weeks and the median number of trastuzumab infusions administered was eight.

Table 5. Adverse Reactions (All Grades ≥ 5% or Grade 3-4 ≥ 1% between Arms) in ToGA
Adverse Reactions | Trastuzumab + FC (N = 294) % |  | FC (N = 290) %
Adverse Reactions | All Grades | Grades 3-4 | All Grades | Grades 3-4
Investigations
Neutropenia | 78 | 34 | 73 | 29
Hypokalemia | 28 | 10 | 24 | 6
Anemia | 28 | 12 | 21 | 10
Thrombocytopenia | 16 | 5 | 11 | 3
Blood and Lymphatic System Disorders
Febrile Neutropenia | –– | 5 | –– | 3
Gastrointestinal Disorders
Diarrhea | 37 | 9 | 28 | 4
Stomatitis | 24 | 1 | 15 | 2
Dysphagia | 6 | 2 | 3 | < 1
General
Fatigue | 35 | 4 | 28 | 2
Fever | 18 | 1 | 12 | 0
Mucosal Inflammation | 13 | 2 | 6 | 1
Chills | 8 | < 1 | 0 | 0
Metabolism and Nutrition Disorders
Weight Decrease | 23 | 2 | 14 | 2
Infections and Infestations
Upper Respiratory Tract Infections | 19 | 0 | 10 | 0
Nasopharyngitis | 13 | 0 | 6 | 0
Renal and Urinary Disorders
Renal Failure and Impairment | 18 | 3 | 15 | 2
Nervous System Disorders
Dysgeusia | 10 | 0 | 5 | 0

The following subsections provide additional detail regarding adverse reactions observed in clinical trials of adjuvant breast cancer, metastatic breast cancer, metastatic gastric cancer, or post-marketing experience.

Cardiomyopathy

Serial measurement of cardiac function (LVEF) was obtained in clinical trials in the adjuvant treatment of breast cancer. In HERA, the median duration of follow-up was12.6 months (12.4 months in the observation arm; 12.6 months in the 1-year trastuzumab arm); and in NSABP B31 and NCCTG N9831, 7.9 years in the AC-T arm, 8.3 years in the AC-TH arm.

Following initiation of trastuzumab therapy, the incidence of new-onset dose-limiting myocardial dysfunction was higher among patients receiving trastuzumab and paclitaxel as compared to those receiving paclitaxel alone in NSABP B31 and NCCTG N9831, and in patients receiving one-year trastuzumab monotherapy compared to observation in HERA (see Table 6, Figures 1 and 2). The incidence of new-onset cardiac dysfunction, as measured by LVEF, remained similar when compared to the analysis performed at a median follow-up of 2.0 years in the AC-TH arm. This analysis showed evidence of reversibility of left ventricular dysfunction, with 64.5% of patients who experienced symptomatic CHF in the AC-TH group being asymptomatic at latest follow-up, and 90.3% having full or partial LVEF recovery.

Table 6 [For NSABP B31, NCCTG N9831 and HERA, events are counted from the beginning of trastuzumab treatment. For BCIRG006, events are counted from the date of randomization.] . Myocardial Dysfunction (by LVEF) in NSABP B31, NCCTG N9831, HERA and BCIRG006
Study and Arm | LVEF < 50% and Decrease from Baseline |  |  | LVEF Decrease
Study and Arm | LVEF < 50% | ≥ 10% decrease | ≥ 16% decrease | < 20% and ≥ 10% | ≥ 20%
NSABP B31 & NCCTG N9831 [NSABP B31 and NCCTG N9831 regimens: doxorubicin and cyclophosphamide followed by paclitaxel (AC→T) or paclitaxel plus trastuzumab (AC→TH).] , [Median duration of follow-up for NSABP B31 and NCCTG N9831 combined was 8.3 years in the AC→TH arm.]
AC→TH (n = 1856) | 23.1% (428) | 18.5% (344) | 11.2% (208) | 37.9% (703) | 8.9% (166)
AC→T (n = 1170) | 11.7% (137) | 7.0% (82) | 3.0% (35) | 22.1% (259) | 3.4% (40)
HERA [Median follow-up duration of 12.6 months in the one-year trastuzumab treatment arm.]
Trastuzumab (n = 1678) | 8.6% (144) | 7.0% (118) | 3.8% (64) | 22.4% (376) | 3.5% (59)
Observation (n = 1708) | 2.7% (46) | 2.0% (35) | 1.2% (20) | 11.9% (204) | 1.2% (21)
BCIRG006 [BCIRG006 regimens: doxorubicin and cyclophosphamide followed by docetaxel (AC→T) or docetaxel plus trastuzumab (AC→TH); docetaxel and carboplatin plus trastuzumab (TCH).]
TCH (n = 1056) | 8.5% (90) | 5.9% (62) | 3.3% (35) | 34.5% (364) | 6.3% (67)
AC→TH (n = 1068) | 17% (182) | 13.3% (142) | 9.8% (105) | 44.3% (473) | 13.2% (141)
AC→T (n = 1050) | 9.5% (100) | 6.6% (69) | 3.3% (35) | 34% (357) | 5.5% (58)

Figure 1. NSABP B31 and NCCTG N9831: Cumulative Incidence of Time to First LVEF Decline of ≥ 10 Percentage Points from Baseline and to Below 50% with Death as a Competing Risk Event

Time 0 is initiation of paclitaxel or trastuzumab + paclitaxel therapy.

Figure 2. HERA: Cumulative Incidence of Time to First LVEF Decline of ≥ 10 Percentage Points from Baseline and to Below 50% with Death as a Competing Risk Event

Time 0 is the date of randomization.

Figure 3. BCIRG006: Cumulative Incidence of Time to First LVEF Decline of ≥ 10 Percentage Points from Baseline and to Below 50% with Death as a Competing Risk Event

Time 0 is the date of randomization.

The incidence of congestive heart failure among patients in the metastatic breast cancer trials was classified for severity using the New York Heart Association classification system (I-IV, where IV is the most severe level of cardiac failure) (see Table 2). In the metastatic breast cancer trials, the probability of cardiac dysfunction was highest in patients who received trastuzumab concurrently with anthracyclines.

In ToGA, 5% of patients in the trastuzumab plus chemotherapy arm compared to 1.1% of patients in the chemotherapy alone arm had LVEF value below 50% with a ≥ 10% absolute decrease in LVEF from pre-treatment values.

Infusion Reactions

During the first infusion with trastuzumab, the symptoms most commonly reported were chills and fever, occurring in approximately 40% of patients in clinical trials. Symptoms were treated with acetaminophen, diphenhydramine, and meperidine (with or without reduction in the rate of trastuzumab infusion); permanent discontinuation of trastuzumab for infusion reactions was required in < 1% of patients. Other signs and/or symptoms may include nausea, vomiting, pain (in some cases at tumor sites), rigors, headache, dizziness, dyspnea, hypotension, elevated blood pressure, rash, and asthenia. Infusion reactions occurred in 21% and 35% of patients, and were severe in 1.4% and 9% of patients, on second or subsequent trastuzumab infusions administered as monotherapy or in combination with chemotherapy, respectively. In the post-marketing setting, severe infusion reactions, including hypersensitivity, anaphylaxis, and angioedema have been reported.

Anemia

In randomized controlled clinical trials, the overall incidence of anemia (30% vs. 21% [H0648g]), of selected NCI-CTC Grade 2–5 anemia (12.3% vs. 6.7% [NSABP B31]), and of anemia requiring transfusions (0.1% vs. 0 patients [NCCTG N9831]) were increased in patients receiving trastuzumab and chemotherapy compared with those receiving chemotherapy alone. Following the administration of trastuzumab as a single agent (H0649g), the incidence of NCI-CTC Grade 3 anemia was < 1%. In ToGA (metastatic gastric cancer), on the trastuzumab-containing arm as compared to the chemotherapy alone arm, the overall incidence of anemia was 28% compared to 21% and of NCI-CTC Grade 3/4 anemia was 12.2% compared to 10.3%.

Neutropenia

In randomized controlled clinical trials in the adjuvant setting, the incidence of selected NCI-CTC Grade 4–5 neutropenia (1.7% vs. 0.8% [NCCTG N9831]) and of selected Grade 2-5 neutropenia (6.4% vs. 4.3% [NSABP B31]) were increased in patients receiving trastuzumab and chemotherapy compared with those receiving chemotherapy alone. In a randomized, controlled trial in patients with metastatic breast cancer, the incidences of NCI-CTC Grade 3/4 neutropenia (32% vs. 22%) and of febrile neutropenia (23% vs. 17%) were also increased in patients randomized to trastuzumab in combination with myelosuppressive chemotherapy as compared to chemotherapy alone. In ToGA (metastatic gastric cancer) on the trastuzumab-containing arm as compared to the chemotherapy alone arm, the incidence of NCI-CTC Grade 3/4 neutropenia was 36.8% compared to 28.9%; febrile neutropenia 5.1% compared to 2.8%.

Infection

The overall incidences of infection (46% vs. 30% [H0648g]), of selected NCI-CTC Grade 2–5 infection/febrile neutropenia (24.3% vs. 13.4% [NSABP B31]) and of selected Grade 3–5 infection/febrile neutropenia (2.9% vs. 1.4%) [NCCTG N9831]) were higher in patients receiving trastuzumab and chemotherapy compared with those receiving chemotherapy alone. The most common site of infections in the adjuvant setting involved the upper respiratory tract, skin, and urinary tract.

In BCIRG006, the overall incidence of infection was higher with the addition of trastuzumab to AC-T but not to TCH [44% (AC-TH), 37% (TCH), 38% (AC-T)]. The incidences of NCI-CTC Grade 3-4 infection were similar [25% (AC-TH), 21% (TCH), 23% (AC-T)] across the three arms.

In a randomized, controlled trial in treatment of metastatic breast cancer, the reported incidence of febrile neutropenia was higher (23% vs. 17%) in patients receiving trastuzumab in combination with myelosuppressive chemotherapy as compared to chemotherapy alone.

Pulmonary Toxicity

Adjuvant Breast Cancer

Among women receiving adjuvant therapy for breast cancer, the incidence of selected NCI-CTC Grade 2-5 pulmonary toxicity (14.3% vs. 5.4% [NSABP B31]) and of selected NCI-CTC Grade 3–5 pulmonary toxicity and spontaneous reported Grade 2 dyspnea (3.4% vs. 0.9% [NCCTG N9831]) was higher in patients receiving trastuzumab and chemotherapy compared with chemotherapy alone. The most common pulmonary toxicity was dyspnea (NCI-CTC Grade 2–5: 11.8% vs. 4.6% [NSABP B31]; NCI-CTC Grade 2–5: 2.4% vs. 0.2% [NCCTG N9831]).

Pneumonitis/pulmonary infiltrates occurred in 0.7% of patients receiving trastuzumab compared with 0.3% of those receiving chemotherapy alone. Fatal respiratory failure occurred in 3 patients receiving trastuzumab, one as a component of multi-organ system failure, as compared to 1 patient receiving chemotherapy alone.

In HERA, there were 4 cases of interstitial pneumonitis in the one-year trastuzumab treatment arm compared to none in the observation arm at a median follow-up duration of 12.6 months.

Metastatic Breast Cancer

Among women receiving trastuzumab for treatment of metastatic breast cancer, the incidence of pulmonary toxicity was also increased. Pulmonary adverse events have been reported in the post-marketing experience as part of the symptom complex of infusion reactions. Pulmonary events include bronchospasm, hypoxia, dyspnea, pulmonary infiltrates, pleural effusions, non-cardiogenic pulmonary edema, and acute respiratory distress syndrome. For a detailed description, [see Warnings and Precautions (5.4)].

Thrombosis/Embolism

In 4 randomized, controlled clinical trials, the incidence of thrombotic adverse events was higher in patients receiving trastuzumab and chemotherapy compared to chemotherapy alone in three studies (2.6% vs. 1.5% [NSABP B31], 2.5% and 3.7% vs. 2.2% [BCIRG006] and 2.1% vs. 0% [H0648g]).

Diarrhea

Among women receiving adjuvant therapy for breast cancer, the incidence of NCI-CTC Grade 2–5 diarrhea (6.7% vs. 5.4% [NSABP B31]) and of NCI-CTC Grade 3–5 diarrhea (2.2% vs. 0% [NCCTG N9831]), and of Grade 1–4 diarrhea (7% vs. 1% [HERA; one-year trastuzumab treatment at 12.6 months median duration of follow-up]) were higher in patients receiving trastuzumab as compared to controls. In BCIRG006, the incidence of Grade 3–4 diarrhea was higher [5.7% AC-TH, 5.5% TCH vs. 3.0% AC-T] and of Grade 1–4 was higher [51% AC-TH, 63% TCH vs. 43% AC-T] among women receiving trastuzumab. Of patients receiving trastuzumab as a single agent for the treatment of metastatic breast cancer, 25% experienced diarrhea. An increased incidence of diarrhea was observed in patients receiving trastuzumab in combination with chemotherapy for treatment of metastatic breast cancer.

Renal Toxicity

In ToGA (metastatic gastric cancer) on the trastuzumab-containing arm as compared to the chemotherapy alone arm the incidence of renal impairment was 18% compared to 14.5%. Severe (Grade 3/4) renal failure was 2.7% on the trastuzumab-containing arm compared to 1.7% on the chemotherapy only arm. Treatment discontinuation for renal insufficiency/failure was 2% on the trastuzumab-containing arm and 0.3% on the chemotherapy only arm.

In the post-marketing setting, rare cases of nephrotic syndrome with pathologic evidence of glomerulopathy have been reported. The time to onset ranged from 4 months to approximately 18 months from initiation of trastuzumab therapy. Pathologic findings included membranous glomerulonephritis, focal glomerulosclerosis, and fibrillary glomerulonephritis. Complications included volume overload and congestive heart failure.

6.2 Post-Marketing Experience

The following adverse reactions have been identified during post-approval use of trastuzumab products. Because these reactions are reported voluntarily from a population of uncertain size, it is not always possible to reliably estimate their frequency or establish a causal relationship to drug exposure.

- Infusion reaction [see Warnings and Precautions (5.2)]
- Oligohydramnios or oligohydramnios sequence, including pulmonary hypoplasia, skeletal abnormalities, and neonatal death [see Warnings and Precautions (5.3)]
- Glomerulopathy [see Adverse Reactions (6.1)]
- Immune thrombocytopenia
- Tumor lysis syndrome (TLS): Cases of possible TLS have been reported in patients treated with trastuzumab products. Patients with significant tumor burden (e.g. bulky metastases) may be at a higher risk. Patients could present with hyperuricemia, hyperphosphatemia, and acute renal failure which may represent possible TLS. Providers should consider additional monitoring and/or treatment as clinically indicated.

7 DRUG INTERACTIONS

Anthracyclines

Patients who receive anthracycline after stopping trastuzumab products may be at increased risk of cardiac dysfunction because of trastuzumab products estimated long washout period [see Clinical Pharmacology (12.3)]. If possible, avoid anthracycline-based therapy for up to 7 months after stopping trastuzumab products. If anthracyclines are used, closely monitor the patient's cardiac function.

8 USE IN SPECIFIC POPULATIONS

8.1 Pregnancy

Risk Summary

Trastuzumab products can cause fetal harm when administered to a pregnant woman. In post-marketing reports and published literature, use of trastuzumab products during pregnancy resulted in cases of oligohydramnios and of oligohydramnios sequence, manifesting as pulmonary hypoplasia, skeletal abnormalities, and neonatal death [see Data]. Apprise the patient of the potential risks to a fetus. There are clinical considerations if a trastuzumab product is used in a pregnant woman or if a patient becomes pregnant within 7 months following the last dose of a trastuzumab product [see Clinical Considerations].

The background risk of major birth defects and miscarriage for the indicated population is unknown. In the U.S. general population, the estimated background risk of major birth defects and miscarriage in clinically recognized pregnancies is 2% to 4% and 15% to 20%, respectively.

Clinical Considerations

Fetal/Neonatal Adverse Reactions

Monitor women who received KANJINTI during pregnancy or within 7 months prior to conception for oligohydramnios. If oligohydramnios occurs, perform fetal/neonatal testing that is appropriate for gestational age and consistent with community standards of care.

Data

Human Data

In post-marketing reports and published literature, use of trastuzumab products during pregnancy resulted in cases of oligohydramnios and of oligohydramnios sequence. Fetal manifestations included pulmonary hypoplasia, skeletal abnormalities and neonatal death. These case reports described oligohydramnios in pregnant women who received trastuzumab either alone or in combination with chemotherapy. In most reported cases, amniotic fluid index increased after trastuzumab was stopped. In reported cases where trastuzumab therapy was resumed after amniotic index improved, oligohydramnios recurred.

Animal Data

In studies where trastuzumab was administered to pregnant Cynomolgus monkeys during the period of organogenesis at doses up to 25 mg/kg given twice weekly (up to 25 times the recommended weekly human dose of 2 mg/kg), trastuzumab crossed the placental barrier during the early (Gestation Days 20 to 50) and late (Gestation Days 120 to 150) phases of gestation. The resulting concentrations of trastuzumab in fetal serum and amniotic fluid were approximately 33% and 25%, respectively, of those present in the maternal serum but were not associated with adverse developmental effects.

8.2 Lactation

Risk Summary

There is no information regarding the presence of trastuzumab products in human milk, the effects on the breastfed infant, or the effects on milk production. Published data suggest human IgG is present in human milk but does not enter the neonatal and infant circulation in substantial amounts.

Trastuzumab was present in the milk of lactating Cynomolgus monkeys but not associated with neonatal toxicity [see Data]. Consider the developmental and health benefits of breastfeeding along with the mother's clinical need for KANJINTI treatment and any potential adverse effects on the breastfed child from KANJINTI or from the underlying maternal condition. This consideration should also take into account the trastuzumab product wash out period of 7 months [see Clinical Pharmacology (12.3)].

Data

In lactating Cynomolgus monkeys, trastuzumab was present in breast milk at about 0.3% of maternal serum concentrations after pre- (beginning Gestation Day 120) and post-partum (through Post-partum Day 28) doses of 25 mg/kg administered twice weekly (25 times the recommended weekly human dose of 2 mg/kg of trastuzumab products). Infant monkeys with detectable serum levels of trastuzumab did not exhibit any adverse effects on growth or development from birth to 1 month of age.

8.3 Females and Males of Reproductive Potential

Pregnancy Testing

Verify the pregnancy status of females of reproductive potential prior to the initiation of KANJINTI.

Contraception

Females

Trastuzumab products can cause embryo-fetal harm when administered during pregnancy.

Advise females of reproductive potential to use effective contraception during treatment with KANJINTI and for 7 months following the last dose of KANJINTI [see Use in Specific Populations (8.1) and Clinical Pharmacology (12.3)].

8.4 Pediatric Use

The safety and effectiveness of KANJINTI in pediatric patients have not been established.

8.5 Geriatric Use

Trastuzumab has been administered to 386 patients who were 65 years of age or over (253 in the adjuvant treatment and 133 in metastatic breast cancer treatment settings). The risk of cardiac dysfunction was increased in geriatric patients as compared to younger patients in both those receiving treatment for metastatic disease in H0648g and H0649g, or adjuvant therapy in NSABP B31 and NCCTG N9831. Limitations in data collection and differences in study design of the 4 studies of trastuzumab in adjuvant treatment of breast cancer preclude a determination of whether the toxicity profile of trastuzumab in older patients is different from younger patients. The reported clinical experience is not adequate to determine whether the efficacy improvements (ORR, TTP, OS, DFS) of trastuzumab treatment in older patients is different from that observed in patients < 65 years of age for metastatic disease and adjuvant treatment.

In ToGA (metastatic gastric cancer), of the 294 patients treated with trastuzumab, 108 (37%) were 65 years of age or older, while 13 (4.4%) were 75 and over. No overall differences in safety or effectiveness were observed.

11 DESCRIPTION

Trastuzumab-anns is a humanized IgG1 kappa monoclonal antibody that selectively binds with high affinity to the extracellular domain of the human epidermal growth factor receptor 2 protein, HER2.

Trastuzumab-anns is produced by recombinant DNA technology in a mammalian cell (Chinese Hamster Ovary) culture containing the antibiotic geneticin. Geneticin is not detectable in the final product.

KANJINTI (trastuzumab-anns) for injection is a sterile, white to pale yellow, preservative-free lyophilized powder with a cake-like appearance, for intravenous administration.

Each multiple-dose vial of KANJINTI delivers 420 mg trastuzumab-anns, 381.8 mg α,α-trehalose dihydrate, 9.5 mg L-histidine HCl monohydrate, 6.1 mg L-histidine, and 1.7 mg polysorbate 20. Reconstitution with 20 mL of the appropriate diluent (BWFI or SWFI) yields a solution containing 21 mg/mL trastuzumab-anns that delivers 20 mL (420 mg trastuzumab-anns), at a pH of approximately 6. If KANJINTI is reconstituted with SWFI without preservative, the reconstituted solution is considered single-dose.

Each single-dose vial of KANJINTI delivers 150 mg trastuzumab-anns, 136.2 mg α,α-trehalose dihydrate, 3.4 mg L-histidine HCl monohydrate, 2.2 mg L-histidine, and 0.6 mg polysorbate 20. Reconstitution with 7.4 mL of Sterile Water for Injection (SWFI) yields a solution containing 21 mg/mL trastuzumab-anns that delivers 7.15 mL (150 mg trastuzumab-anns), at a pH of approximately 6.

12 CLINICAL PHARMACOLOGY

12.1 Mechanism of Action

The HER2 (or c-erbB2) proto-oncogene encodes a transmembrane receptor protein of 185 kDa, which is structurally related to the epidermal growth factor receptor. Trastuzumab products have been shown, in both in vitro assays and in animals, to inhibit the proliferation of human tumor cells that overexpress HER2.

Trastuzumab products are mediators of antibody-dependent cellular cytotoxicity (ADCC). In vitro, trastuzumab product-mediated ADCC has been shown to be preferentially exerted on HER2-overexpressing cancer cells compared with cancer cells that do not overexpress HER2.

12.2 Pharmacodynamics

Trastuzumab product exposure-response relationships and the time course of pharmacodynamic responses are not fully characterized.

Cardiac Electrophysiology

The effects of trastuzumab on electrocardiographic (ECG) endpoints, including QTc interval duration, were evaluated in patients with HER2 positive solid tumors. Trastuzumab had no clinically relevant effect on the QTc interval duration and there was no apparent relationship between serum trastuzumab concentrations and change in QTcF interval duration in patients with HER2 positive solid tumors.

12.3 Pharmacokinetics

The pharmacokinetics of trastuzumab was evaluated in a pooled population pharmacokinetic (PK) model analysis of 1582 subjects with primarily breast cancer and metastatic gastric cancer (MGC) receiving intravenous trastuzumab. Total trastuzumab clearance increases with decreasing concentrations due to parallel linear and non-linear elimination pathways.

Although the average trastuzumab exposure was higher following the first cycle in breast cancer patients receiving the once every three week schedule compared to the weekly schedule of trastuzumab, the average steady-state exposure was essentially the same at both dosages. The average trastuzumab exposure following the first cycle and at steady-state as well as the time to steady-state was higher in breast cancer patients compared to MGC patients at the same dosage; however, the reason for this exposure difference is unknown. Additional predicted trastuzumab exposure and PK parameters following the first trastuzumab cycle and at steady-state exposure are described in Tables 7 and 8, respectively.

Population PK based simulations indicate that following discontinuation of trastuzumab, concentrations in at least 95% of breast cancer and MGC patients will decrease to approximately 3% of the population predicted steady-state trough serum concentration (approximately 97% washout) by 7 months [see Warnings and Precautions (5.1) and Use in Specific Populations (8.1, 8.3)].

Table 7. Population Predicted Cycle 1 PK Exposures (Median with 5th - 95th Percentiles) in Breast Cancer and MGC Patients
Schedule | Primary tumor type | N | Cmin (µg/mL) | Cmax (µg/mL) | AUC0 - 21days (µg.day/mL)
8 mg/kg + 6 mg/kg q3w | Breast cancer | 1195 | 29.4 (5.8 - 59.5) | 178 (117 - 291) | 1373 (736 - 2245)
8 mg/kg + 6 mg/kg q3w | MGC | 274 | 23.1 (6.1 - 50.3) | 132 (84.2 - 225) | 1109 (588 - 1938)
4 mg/kg + 2 mg/kg qw | Breast cancer | 1195 | 37.7 (12.3 - 70.9) | 88.3 (58 - 144) | 1066 (586 - 1754)

Table 8. Population Predicted Steady-State PK Exposures (Median with 5th - 95th Percentiles) in Breast Cancer and MGC Patients
Schedule | Primary tumor type | N | Cmin,ss [Steady-state trough serum concentration of trastuzumab.] (µg/mL) | Cmax,ss [Maximum steady-state serum concentration of trastuzumab.] (µg/mL) | AUCss, 0-21 days (µg.day/mL) | Time to steady-state (week) | Total CL range at steady-state (L/day)
8 mg/kg + 6 mg/kg q3w | Breast cancer | 1195 | 47.4 (5 - 115) | 179 (107 - 309) | 1794 (673 - 3618) | 12 | 0.173 - 0.283
8 mg/kg + 6 mg/kg q3w | MGC | 274 | 32.9 (6.1 - 88.9) | 131 (72.5 - 251) | 1338 (557 - 2875) | 9 | 0.189 - 0.337
4 mg/kg + 2 mg/kg qw | Breast cancer | 1195 | 66.1 (14.9 - 142) | 109 (51.0 - 209) | 1765 (647 - 3578) | 12 | 0.201 - 0.244

Specific Populations: Based on a population pharmacokinetic analysis, no clinically significant differences were observed in the pharmacokinetics of trastuzumab based on age (< 65 (n = 1294); ≥ 65 (n = 288)), race (Asian (n = 264); non-Asian (n = 1324)) and renal impairment (mild (creatinine clearance [CLcr] 60 to 90 mL/min) (n = 636) or moderate (CLcr 30 to 60 mL/min) (n = 133). The pharmacokinetics of trastuzumab products in patients with severe renal impairment, end-stage renal disease with or without hemodialysis, or hepatic impairment is unknown.

Drug Interaction Studies:

There have been no formal drug interaction studies performed with trastuzumab products in humans. Clinically significant interactions between trastuzumab and concomitant medications used in clinical trials have not been observed.

Paclitaxel and doxorubicin: Concentrations of paclitaxel and doxorubicin and their major metabolites (i.e., 6-α hydroxyl-paclitaxel [POH], and doxorubicinol [DOL], respectively) were not altered in the presence of trastuzumab when used as combination therapy in clinical trials. Trastuzumab concentrations were not altered as part of this combination therapy.

Docetaxel and carboplatin: When trastuzumab was administered in combination with docetaxel or carboplatin, neither the plasma concentrations of docetaxel or carboplatin nor the plasma concentrations of trastuzumab were altered.

Cisplatin and capecitabine: In a drug interaction substudy conducted in patients in ToGA, the pharmacokinetics of cisplatin, capecitabine and their metabolites were not altered when administered in combination with trastuzumab.

12.6 Immunogenicity

The observed incidence of anti-drug antibodies is highly dependent on the sensitivity and specificity of the assay. Differences in assay methods preclude meaningful comparisons of the incidence of anti-drug antibodies in the studies described below with the incidence of anti-drug antibodies in other studies, including those of trastuzumab or of other trastuzumab products.

Among 903 women with metastatic breast cancer, human anti-human antibody (HAHA) to trastuzumab was detected in one patient using an enzyme linked immunosorbent assay (ELISA). This patient did not experience an allergic reaction. Samples for assessment of HAHA were not collected in studies of adjuvant breast cancer.

The clinical relevance of the development of anti-trastuzumab antibodies after treatment with trastuzumab is not known.

13 NONCLINICAL TOXICOLOGY

13.1 Carcinogenesis, Mutagenesis, Impairment of Fertility

Trastuzumab products have not been tested for carcinogenic potential.

No evidence of mutagenic activity was observed when trastuzumab was tested in the standard Ames bacterial and human peripheral blood lymphocyte mutagenicity assays, at concentrations of up to 5000 µg/mL. In an in vivo micronucleus assay, no evidence of chromosomal damage to mouse bone marrow cells was observed following bolus intravenous doses of up to 118 mg/kg of trastuzumab.

A fertility study was conducted in female cynomolgus monkeys at doses up to 25 times the weekly recommended human dose of 2 mg/kg of trastuzumab and has revealed no evidence of impaired fertility, as measured by menstrual cycle duration and female sex hormone levels.

14 CLINICAL STUDIES

14.1 Adjuvant Breast Cancer

The safety and efficacy of trastuzumab in women receiving adjuvant chemotherapy for HER2-overexpressing breast cancer were evaluated in an integrated analysis of two randomized, open-label, clinical trials (NSABP B31 and NCCTG N9831) with a total of 4063 women at the protocol-specified final overall survival analysis, a third randomized, open-label, clinical trial (HERA) with a total of 3386 women at definitive Disease-Free Survival analysis for one-year trastuzumab treatment versus observation, and a fourth randomized, open-label clinical trial with a total of 3222 patients (BCIRG006).

NSABP B31 and NCCTG N9831

In NSABP B31 and NCCTG N9831, breast tumor specimens were required to show HER2 overexpression (3+ by IHC) or gene amplification (by FISH). HER2 testing was verified by a central laboratory prior to randomization (NCCTG N9831) or was required to be performed at a reference laboratory (NSABP B31). Patients with a history of active cardiac disease based on symptoms, abnormal electrocardiographic, radiologic, or left ventricular ejection fraction findings or uncontrolled hypertension (diastolic > 100 mm Hg or systolic > 200 mm Hg) were not eligible.

Patients were randomized (1:1) to receive doxorubicin and cyclophosphamide followed by paclitaxel (AC→paclitaxel) alone or paclitaxel plus trastuzumab (AC→paclitaxel + trastuzumab). In both trials, patients received four 21-day cycles of doxorubicin 60 mg/m^2 and cyclophosphamide 600 mg/m^2.

Paclitaxel was administered either weekly (80 mg/m^2) or every 3 weeks (175 mg/m^2) for a total of 12 weeks in NSABP B31; paclitaxel was administered only by the weekly schedule in NCCTG N9831. Trastuzumab was administered at 4 mg/kg on the day of initiation of paclitaxel and then at a dose of 2 mg/kg weekly for a total of 52 weeks. Trastuzumab treatment was permanently discontinued in patients who developed congestive heart failure, or persistent/recurrent LVEF decline [see Dosage and Administration (2.5)]. Radiation therapy, if administered, was initiated after the completion of chemotherapy. Patients with ER+ and/or PR+ tumors received hormonal therapy. The major efficacy outcome measure of the combined efficacy analysis was Disease-Free Survival (DFS), defined as the time from randomization to recurrence, occurrence of contralateral breast cancer, other second primary cancer, or death. An additional efficacy outcome measure was overall survival (OS).

A total of 3752 patients were included in the joint efficacy analysis of DFS following a median follow-up of 2.0 years in the AC→paclitaxel + trastuzumab arm. The pre-planned final OS analysis from the joint analysis included 4063 patients and was performed when 707 deaths had occurred after a median follow-up of 8.3 years in the AC→paclitaxel + trastuzumab arm. The data from both arms in NSABP B31 and two of the three study arms in NCCTG N9831 were pooled for efficacy analyses.

The patients included in the DFS analysis had a median age of 49 years (range: 22–80 years; 6% > 65 years), 84% were white, 7% black, 4% Hispanic, and 4% Asian/Pacific Islander. Disease characteristics included 90% infiltrating ductal histology, 38% T1, 91% nodal involvement, 27% intermediate and 66% high grade pathology, and 53% ER+ and/or PR+ tumors.

HERA

In HERA, breast tumor specimens were required to show HER2 overexpression (3+ by IHC) or gene amplification (by FISH) as determined at a central laboratory. Patients with node-negative disease were required to have ≥ T1c primary tumor. Patients with a history of congestive heart failure or LVEF < 55%, uncontrolled arrhythmias, angina requiring medication, clinically significant valvular heart disease, evidence of transmural infarction on ECG, poorly controlled hypertension (systolic > 180 mm Hg or diastolic > 100 mm Hg) were not eligible.

Patients were randomized (1:1:1) upon completion of definitive surgery, and at least four cycles of chemotherapy to receive no additional treatment, or one year of trastuzumab treatment or two years of trastuzumab treatment. Patients undergoing a lumpectomy had also completed standard radiotherapy. Patients with ER+ and/or PgR+ disease received systemic adjuvant hormonal therapy at investigator discretion. Trastuzumab was administered with an initial dose of 8 mg/kg followed by subsequent doses of 6 mg/kg once every three weeks. The major efficacy outcome measure was Disease-Free Survival (DFS), defined as in NSABP B31 and NCCTG N9831.

HERA was designed to compare one and two years of once every three week trastuzumab treatment versus observation in patients with HER2 positive EBC following surgery, established chemotherapy and radiotherapy (if applicable). A protocol specified interim efficacy analysis comparing one-year trastuzumab treatment to observation was performed at a median follow-up duration of 12.6 months in the trastuzumab arm.

Among the 3386 patients randomized to the observation (n = 1693) and trastuzumab one-year (n = 1693) treatment arms, the median age was 49 years (range: 21–80), 83% were White, and 13% were Asian. Disease characteristics: 94% infiltrating ductal carcinoma, 50% ER+ and/or PgR+, 57% node positive, 32% node negative, and in 11% of patients, nodal status was not assessable due to prior neo-adjuvant chemotherapy. Ninety-six percent (1055/1098) of patients with node-negative disease had high risk features: among the 1098 patients with node-negative disease, 49% (543) were ER− and PgR−, and 47% (512) were ER and/or PgR + and had at least one of the following high risk features: pathological tumor size greater than 2 cm, Grade 2–3, or age < 35 years. Prior to randomization, 94% of patients had received anthracycline-based chemotherapy regimens.

After the DFS results comparing observation to one-year trastuzumab treatment were disclosed, a prospectively planned analysis that included comparison of one year versus two years of trastuzumab treatment at a median follow-up duration of 8 years was performed. Based on this analysis, extending trastuzumab treatment for a duration of two years did not show additional benefit over treatment for one year [Hazard Ratios of two-years trastuzumab versus one-year trastuzumab treatment in the intent to treat (ITT) population for Disease-Free Survival (DFS) = 0.99 (95% CI: 0.87, 1.13), p-value = 0.90 and Overall Survival (OS) = 0.98 (0.83, 1.15); p-value = 0.78].

BCIRG006

In BCIRG006, breast tumor specimens were required to show HER2 gene amplification (FISH+ only) as determined at a central laboratory. Patients were required to have either node-positive disease, or node-negative disease with at least one of the following high-risk features: ER/PR-negative, tumor size > 2 cm, age < 35 years, or histologic and/or nuclear Grade 2 or 3. Patients with a history of CHF, myocardial infarction, Grade 3 or 4 cardiac arrhythmia, angina requiring medication, clinically significant valvular heart disease, poorly controlled hypertension (diastolic > 100 mm Hg), any T4 or N2 or known N3 or M1 breast cancer were not eligible.

Patients were randomized (1:1:1) to receive doxorubicin and cyclophosphamide followed by docetaxel (AC-T), doxorubicin and cyclophosphamide followed by docetaxel plus trastuzumab (AC-TH), or docetaxel and carboplatin plus trastuzumab (TCH). In both the AC-T and AC-TH arms, doxorubicin 60 mg/m^2 and cyclophosphamide 600 mg/m^2 were administered every 3 weeks for four cycles; docetaxel 100 mg/m^2 was administered every 3 weeks for four cycles. In the TCH arm, docetaxel 75 mg/m^2 and carboplatin (at a target AUC of 6 mg/mL/min as a 30- to 60-minute infusion) were administered every 3 weeks for six cycles. Trastuzumab was administered weekly (initial dose of 4 mg/kg followed by weekly dose of 2 mg/kg) concurrently with either T or TC, and then every 3 weeks (6 mg/kg) as monotherapy for a total of 52 weeks. Radiation therapy, if administered, was initiated after completion of chemotherapy. Patients with ER+ and/or PR+ tumors received hormonal therapy. Disease-Free Survival (DFS) was the major efficacy outcome measure.

Among 3222 patients, the median age was 49 (range: 22 to 74 years; 6% ≥ 65 years). Disease characteristics included 54% ER+ and/or PR+ and 71% node positive. Prior to randomization, all patients underwent primary surgery for breast cancer.

The results for DFS for the integrated analysis of NSABP B31 and NCCTG N9831, HERA, and BCIRG006 and OS results for the integrated analysis of NSABP B31 and NCCTG N9831, and HERA are presented in Table 9. For NSABP B31 and NCCTG N9831, the duration of DFS following a median follow-up of 2.0 years in the AC→TH arm is presented in Figure 4, and the duration of OS after a median follow-up of 8.3 years in the AC→TH arm is presented in Figure 5. The duration of DFS for BCIRG006 is presented in Figure 6. For NSABP B31 and NCCTG N9831, the OS hazard ratio was 0.64 (95% CI: 0.55, 0.74). At 8.3 years of median follow-up [AC→TH], the survival rate was estimated to be 86.9% in the AC→TH arm and 79.4% in the AC→T arm. The final OS analysis results from NSABP B31 and NCCTG N9831 indicate that OS benefit by age, hormone receptor status, number of positive lymph nodes, tumor size and grade, and surgery/radiation therapy was consistent with the treatment effect in the overall population. In patients ≤ 50 years of age (n = 2197), the OS hazard ratio was 0.65 (95% CI: 0.52, 0.81) and in patients > 50 years of age (n = 1866), the OS hazard ratio was 0.63 (95% CI: 0.51, 0.78). In the subgroup of patients with hormone receptor-positive disease (ER-positive and/or PR-positive) (n = 2223), the hazard ratio for OS was 0.63 (95% CI: 0.51, 0.78). In the subgroup of patients with hormone receptor-negative disease (ER-negative and PR-negative) (n = 1830), the hazard ratio for OS was 0.64 (95% CI: 0.52, 0.80). In the subgroup of patients with tumor size ≤ 2 cm (n = 1604), the hazard ratio for OS was 0.52 (95% CI: 0.39, 0.71). In the subgroup of patients with tumor size > 2 cm (n = 2448), the hazard ratio for OS was 0.67 (95% CI: 0.56, 0.80).

Table 9. Efficacy Results from Adjuvant Treatment of Breast Cancer (NSABP B31 and NCCTG N9831, HERA, and BCIRG006)
 | DFS events | DFS Hazard ratio (95% CI) p-value | Deaths (OS events) | OS Hazard ratio p-value
NSABP B31 and NCCTG N9831 [NSABP B31 and NCCTG N9831 regimens: doxorubicin and cyclophosphamide followed by paclitaxel (AC→T) or paclitaxel plus trastuzumab (AC→TH).]
AC→TH (n = 1872) [Efficacy evaluable population, for the primary DFS analysis, following a median follow-up of 2.0 years in the AC→TH arm.] (n = 2031) [Efficacy evaluable population, for the final OS analysis, following 707 deaths (8.3 years of median follow-up in the AC→TH arm).] | 133 | 0.48, [Hazard ratio estimated by Cox regression stratified by clinical trial, intended paclitaxel schedule, number of positive nodes, and hormone receptor status.] (0.39, 0.59) p ˂ 0.0001 [stratified log-rank test.] | 289 | 0.64, (0.55, 0.74) p ˂ 0.0001
AC→T (n = 1880) (n = 2032) | 261 |  | 418
HERA [At definitive DFS analysis with median duration of follow-up of 12.6 months in the one-year trastuzumab treatment arm.]
Chemo→Trastuzumab (n = 1693) | 127 | 0.54 (0.44, 0.67) p ˂ 0.0001 [log-rank test.] | 31 | 0.75 p = NS [NS = non-significant.]
Chemo→ Observation (n = 1693) | 219 |  | 40
BCIRG006 [BCIRG006 regimens: doxorubicin and cyclophosphamide followed by docetaxel (AC→T) or docetaxel plus trastuzumab (AC→TH); docetaxel and carboplatin plus trastuzumab (TCH).]
TCH (n = 1075) | 134 | 0.67 (0.54 – 0.84) p = 0.0006, [A two-sided alpha level of 0.025 for each comparison.] | 56
AC→TH (n = 1074) | 121 | 0.60 (0.48 – 0.76) p < 0.0001, | 49
AC→T (n = 1073) | 180 |  | 80
CI = confidence interval.

Figure 4. Duration of Disease-Free Survival in Patients with Adjuvant Treatment of Breast Cancer (NSABP B31 and NCCTG N9831)

Figure 5. Overall Survival in Patients with Adjuvant Treatment of Breast Cancer (NSABP B31 and NCCTG N9831)

Figure 6. Disease-Free Survival in Patients with Adjuvant Treatment of Breast Cancer (BCIRG006)

Exploratory analyses of DFS as a function of HER2 overexpression or gene amplification were conducted for patients in NCCTG N9831 and HERA, where central laboratory testing data were available. The results are shown in Table 10. The number of events in NCCTG N9831 was small with the exception of the IHC 3+/FISH+ subgroup, which constituted 81% of those with data. Definitive conclusions cannot be drawn regarding efficacy within other subgroups due to the small number of events. The number of events in HERA was adequate to demonstrate significant effects on DFS in the IHC 3+/FISH unknown and the FISH +/IHC unknown subgroups.

Table 10. DFS in NCCTG N9831 and HERA for Patients with HER2 Overexpression or Amplification
 | NCCTG N9831 |  | HERA [Median follow-up duration of 12.6 months in the one-year trastuzumab treatment arm.]
HER2 Assay Result [IHC by HercepTest, FISH by PathVysion (HER2/CEP17 ratio ≥ 2.0) as performed at a central laboratory.] | Number of Patients | Hazard Ratio DFS (95% CI) | Number of Patients | Hazard Ratio DFS (95% CI)
IHC 3+
FISH (+) | 1170 | 0.42 (0.27, 0.64) | 91 | 0.56 (0.13, 2.50)
FISH (–) | 51 | 0.71 (0.04, 11.79) | 8 | –
FISH Unknown | 51 | 0.69 (0.09, 5.14) | 2258 | 0.53 (0.41, 0.69)
IHC < 3+ / FISH (+) | 174 | 1.01 (0.18, 5.65) | 299 [All cases in this category in HERA were IHC 2+.] | 0.53 (0.20, 1.42)
IHC unknown / FISH (+) | – | – | 724 | 0.59 (0.38, 0.93)

14.2 Metastatic Breast Cancer

The safety and efficacy of trastuzumab in treatment of women with metastatic breast cancer were studied in a randomized, controlled clinical trial in combination with chemotherapy (H0648g, n = 469 patients) and an open-label single agent clinical trial (H0649g, n = 222 patients). Both trials studied patients with metastatic breast cancer whose tumors overexpress the HER2 protein. Patients were eligible if they had 2 or 3 levels of overexpression (based on a 0 to 3 scale) by immunohistochemical assessment of tumor tissue performed by a central testing lab.

Previously Untreated Metastatic Breast Cancer (H0648g)

H0648g was a multicenter, randomized, open-label clinical trial conducted in 469 women with metastatic breast cancer who had not been previously treated with chemotherapy for metastatic disease. Tumor specimens were tested by IHC (Clinical Trial Assay, CTA) and scored as 0, 1+, 2+, or 3+, with 3+ indicating the strongest positivity. Only patients with 2+ or 3+ positive tumors were eligible (about 33% of those screened). Patients were randomized to receive chemotherapy alone or in combination with trastuzumab given intravenously as a 4 mg/kg loading dose followed by weekly doses of trastuzumab at 2 mg/kg. For those who had received prior anthracycline therapy in the adjuvant setting, chemotherapy consisted of paclitaxel (175 mg/m^2 over 3 hours every 21 days for at least six cycles); for all other patients, chemotherapy consisted of anthracycline plus cyclophosphamide (AC: doxorubicin 60 mg/m^2 or epirubicin 75 mg/m^2 plus 600 mg/m^2 cyclophosphamide every 21 days for six cycles). Sixty-five percent of patients randomized to receive chemotherapy alone in this study received trastuzumab at the time of disease progression as part of a separate extension study.

Based upon the determination by an independent Response Evaluation Committee the patients randomized to trastuzumab and chemotherapy experienced a significantly longer median time to disease progression (TTP), a higher overall response rate (ORR), and a longer median duration of response (DoR) as compared with patients randomized to chemotherapy alone. Patients randomized to trastuzumab and chemotherapy also had a longer median overall survival (OS) (see Table 11). These treatment effects were observed both in patients who received trastuzumab plus paclitaxel and in those who received trastuzumab plus AC; however, the magnitude of the effects was greater in the paclitaxel subgroup.

Table 11. H0648g: Efficacy Results in First-Line Treatment for Metastatic Breast Cancer
 | Combined Results |  | Paclitaxel Subgroup |  | AC [AC = Anthracycline (doxorubicin or epirubicin) and cyclophosphamide.] Subgroup
 | Trastuzumab + All Chemotherapy (n = 235) | All Chemotherapy (n = 234) | Trastuzumab + Paclitaxel (n = 92) | Paclitaxel (n = 96) | Trastuzumab + AC (n = 143) | AC (n = 138)
Time to Disease Progression (TTP)
Median (months) [Assessed by an independent Response Evaluation Committee.] , [Kaplan-Meier Estimate.] | 7.2 | 4.5 | 6.7 | 2.5 | 7.6 | 5.7
95% CI | 7, 8 | 4, 5 | 5, 10 | 2, 4 | 7, 9 | 5, 7
p-value [log-rank test.] | ˂ 0.0001 |  | ˂ 0.0001 |  | 0.002
Overall Response Rate (ORR)
Events (n) | 45 | 29 | 38 | 15 | 50 | 38
95% CI | 39, 51 | 23, 35 | 28, 48 | 8, 22 | 42, 58 | 30, 46
p-value [Χ^2-test.] | ˂ 0.001 |  | ˂ 0.001 |  | 0.10
Duration of Response (DoR)
Median (months), | 8.3 | 5.8 | 8.3 | 4.3 | 8.4 | 6.4
25%, 75% Quartile | 6, 15 | 4, 8 | 5, 11 | 4, 7 | 6, 15 | 4, 8
Overall Survival (OS)
Median (months) | 25.1 | 20.3 | 22.1 | 18.4 | 26.8 | 21.4
95% CI | 22, 30 | 17, 24 | 17, 29 | 13, 24 | 23, 33 | 18, 27
p-value | 0.05 |  | 0.17 |  | 0.16

Data from H0648g suggest that the beneficial treatment effects were largely limited to patients with the highest level of HER2 protein overexpression (3+) (see Table 12).

Table 12. Treatment Effects in H0648g as a Function of HER2 Overexpression or Amplification
HER2 Assay Result | Number of Patients (N) | Relative Risk [The relative risk represents the risk of progression or death in the trastuzumab plus chemotherapy arm versus the chemotherapy arm.] for Time to Disease Progression (95% CI) | Relative Risk for Mortality (95% CI)
CTA 2+ or 3+ | 469 | 0.49 (0.40, 0.61) | 0.80 (0.64, 1.00)
FISH (+) [FISH testing results were available for 451 of the 469 patients enrolled on study.] | 325 | 0.44 (0.34, 0.57) | 0.70 (0.53, 0.91)
FISH (–) | 126 | 0.62 (0.42, 0.94) | 1.06 (0.70, 1.63)
CTA 2+ | 120 | 0.76 (0.50, 1.15) | 1.26 (0.82, 1.94)
FISH (+) | 32 | 0.54 (0.21, 1.35) | 1.31 (0.53, 3.27)
FISH (–) | 83 | 0.77 (0.48, 1.25) | 1.11 (0.68, 1.82)
CTA 3+ | 349 | 0.42 (0.33, 0.54) | 0.70 (0.51, 0.90)
FISH (+) | 293 | 0.42 (0.32, 0.55) | 0.67 (0.51, 0.89)
FISH (–) | 43 | 0.43 (0.20, 0.94) | 0.88 (0.39, 1.98)

Previously Treated Metastatic Breast Cancer (H0649g)

Trastuzumab was studied as a single agent in a multicenter, open-label, single-arm clinical trial (H0649g) in patients with HER2-overexpressing metastatic breast cancer who had relapsed following one or two prior chemotherapy regimens for metastatic disease. Of 222 patients enrolled, 66% had received prior adjuvant chemotherapy, 68% had received two prior chemotherapy regimens for metastatic disease, and 25% had received prior myeloablative treatment with hematopoietic rescue. Patients were treated with a loading dose of 4 mg/kg IV followed by weekly doses of trastuzumab at 2 mg/kg IV.

The ORR (complete response + partial response), as determined by an independent Response Evaluation Committee, was 14%, with a 2% complete response rate and a 12% partial response rate. Complete responses were observed only in patients with disease limited to skin and lymph nodes. The overall response rate in patients whose tumors tested as CTA 3+ was 18% while in those that tested as CTA 2+, it was 6%.

14.3 Metastatic Gastric Cancer

The safety and efficacy of trastuzumab in combination with cisplatin and a fluoropyrimidine (capecitabine or 5-fluorouracil) were studied in patients previously untreated for metastatic gastric or gastroesophageal junction adenocarcinoma (ToGA). In this open-label, multi-center trial, 594 patients were randomized 1:1 to trastuzumab in combination with cisplatin and a fluoropyrimidine (FC+H) or chemotherapy alone (FC). Randomization was stratified by extent of disease (metastatic vs. locally advanced), primary site (gastric vs. gastroesophageal junction), tumor measurability (yes vs. no), ECOG performance status (0,1 vs. 2), and fluoropyrimidine (capecitabine vs. 5-fluorouracil). All patients were either HER2 gene amplified (FISH+) or HER2-overexpressing (IHC 3+). Patients were also required to have adequate cardiac function (e.g. LVEF > 50%).

On the trastuzumab-containing arm, trastuzumab was administered as an IV infusion at an initial dose of 8 mg/kg followed by 6 mg/kg every 3 weeks until disease progression. On both study arms cisplatin was administered at a dose of 80 mg/m^2 Day 1 every 3 weeks for 6 cycles as a 2 hour IV infusion. On both study arms capecitabine was administered at 1000 mg/m^2 dose orally twice daily (total daily dose 2000 mg/m^2) for 14 days of each 21 day cycle for 6 cycles. Alternatively, continuous intravenous infusion (CIV) 5-fluorouracil was administered at a dose of 800 mg/m^2/day from Day 1 through Day 5 every three weeks for 6 cycles.

The median age of the study population was 60 years (range: 21-83); 76% were male; 53% were Asian, 38% Caucasian, 5% Hispanic, 5% other racial/ethnic groups; 91% had ECOG PS of 0 or 1; 82% had primary gastric cancer and 18% had primary gastroesophageal adenocarcinoma. Of these patients, 23% had undergone prior gastrectomy, 7% had received prior neoadjuvant and/or adjuvant therapy, and 2% had received prior radiotherapy.

The main outcome measure of ToGA was overall survival (OS), analyzed by the unstratified log-rank test. The final OS analysis based on 351 deaths was statistically significant (nominal significance level of 0.0193). An updated OS analysis was conducted at one year after the final analysis. The efficacy results of both the final and the updated analyses are summarized in Table 13 and Figure 7.

Table 13. Overall Survival in ToGA (ITT Population)
 | FC [FC = capecitabine vs. 5-fluorouracil] + Trastuzumab Arm N = 298 | FC Arm N = 296
Overall Survival (interim analysis)
N (%) | 167 (56.0%) | 184 (62.2%)
Median (months) | 13.5 | 11.0
95% CI | (11.7, 15.7) | (9.4, 12.5)
Hazard Ratio | 0.73 (0.60, 0.91) 0.0038
95% CI | 0.73 (0.60, 0.91) 0.0038
p-value [Two sided p-value comparing with the nominal significance level of 0.0193.] | 0.73 (0.60, 0.91) 0.0038
Overall Survival (updated)
N (%) | 221 (74.2%) | 227 (76.7%)
Median (months) | 13.1 | 11.7
95% CI | (11.9, 15.1) | (10.3, 13.0)
Hazard Ratio 95% CI | 0.80 (0.67, 0.97)

Figure 7. Updated Overall Survival in Patients with Metastatic Gastric Cancer (ToGA)

An exploratory analysis of OS in patients based on HER2 gene amplification (FISH) and protein overexpression (IHC) testing is summarized in Table 14.

Table 14. Exploratory Analyses by HER2 Status Using Updated Overall Survival Results
 | FC (N = 296) [Two patients on the FC arm who were FISH+ but IHC status unknown were excluded from the exploratory subgroup analyses.] | FC + H (N = 298) [Five patients on the trastuzumab-containing arm who were FISH+, but IHC status unknown were excluded from the exploratory subgroup analyses.]
FISH+ / IHC 0, 1+ subgroup (N = 133)
No. Deaths / n (%) | 57/71 (80%) | 56/62 (90%)
Median OS Duration (mos.) | 8.8 | 8.3
95% CI (mos.) | (6.4, 11.7) | (6.2, 10.7)
Hazard ratio (95% CI) | 1.33 (0.92, 1.92)
FISH+ / IHC2+ subgroup (N = 160)
No. Deaths / n (%) | 65/80 (81%) | 64/80 (80%)
Median OS Duration (mos.) | 10.8 | 12.3
95% CI (mos.) | (6.8, 12.8) | (9.5, 15.7)
Hazard ratio (95% CI) | 0.78 (0.55, 1.10)
FISH+ or FISH- / IHC 3+ [Includes 6 patients on chemotherapy arm, 10 patients on trastuzumab arm with FISH-, IHC 3+ and 8 patients on chemotherapy arm, 8 patients on trastuzumab arm with FISH status unknown, IHC 3+.] subgroup (N = 294)
No. Deaths / n (%) | 104/143 (73%) | 96/151 (64%)
Median OS Duration (mos.) | 13.2 | 18.0
95% CI (mos.) | (11.5, 15.2) | (15.5, 21.2)
Hazard ratio (95% CI) | 0.66 (0.50, 0.87)

16 HOW SUPPLIED/STORAGE AND HANDLING

420 mg Multiple-dose vial (NDC 55513-132-01, 55513-132-21)

- KANJINTI (trastuzumab-anns) for injection 420 mg/vial is supplied in a multiple-dose vial as a preservative-free, white to pale yellow lyophilized sterile powder, under vacuum. Each carton contains one multiple-dose vial of KANJINTI.

150 mg Single-dose vial (NDC 55513-141-01, 55513-141-21).

- KANJINTI (trastuzumab-anns) for injection 150 mg/vial is supplied in a single-dose vial as a preservative-free, white to pale yellow lyophilized sterile powder, under vacuum. Each carton contains one single-dose vial of KANJINTI.

STORAGE AND HANDLING

Store KANJINTI vials in the original carton to protect from light in the refrigerator at 2°C to 8°C (36°F to 46°F) until time of reconstitution.

17 PATIENT COUNSELING INFORMATION

Cardiomyopathy

- Advise patients to contact a healthcare professional immediately for any of the following: new onset or worsening shortness of breath, cough, swelling of the ankles/legs, swelling of the face, palpitations, weight gain of more than 5 pounds in 24 hours, dizziness or loss of consciousness [see Boxed Warning: Cardiomyopathy].

Embryo-Fetal Toxicity

- Advise pregnant women and females of reproductive potential that KANJINTI exposure during pregnancy or within 7 months prior to conception can result in fetal harm. Advise female patients to contact their healthcare provider with a known or suspected pregnancy [see Use in Specific Populations (8.1)].
- Advise females of reproductive potential to use effective contraception during treatment and for 7 months following the last dose of KANJINTI [see Use in Specific Populations (8.3)].

KANJINTI® (trastuzumab-anns)
Manufactured by:
Amgen Inc.
One Amgen Center Drive
Thousand Oaks, CA 91320-1799
U.S. License No. 1080

Marketed by Amgen Inc.

AMGEN and KANJINTI® (trastuzumab-anns) are trademarks owned or licensed by Amgen Inc., its subsidiaries, or affiliates.

© 2019, 2022, 2024-2025 Amgen Inc. All rights reserved.

1xxxxxx
v5

PRINCIPAL DISPLAY PANEL

NDC 55513-132-01
KANJINTI™
(trastuzumab-anns)
For Injection
420 mg/vial

For intravenous infusion after reconstitution

420 mg/vial

Contents: Each carton contains one 420 mg KANJINTI multiple-dose vial.

AMGEN®

Store vial in the original carton to protect from light in the refrigerator at

2°C to 8°C (36°F to 46°F) until time of reconstitution.

Do not shake. Do not freeze reconstituted solution.

PRINCIPAL DISPLAY PANEL

NDC 55513-141-01

KANJINTI™

(trastuzumab-anns)
For Injection

150 mg/vial

For intravenous infusion only

150 mg/vial

Single-Dose Vial – Discard Unused Portion

Contents: Each carton contains one 150 mg KANJINTI Single-Dose Vial.

AMGEN®

Store vial in the original carton to protect from light in the refrigerator

at 2°C to 8°C (36°F to 46°F) until time of reconstitution.

Do not shake.

Do not freeze reconstituted solution.